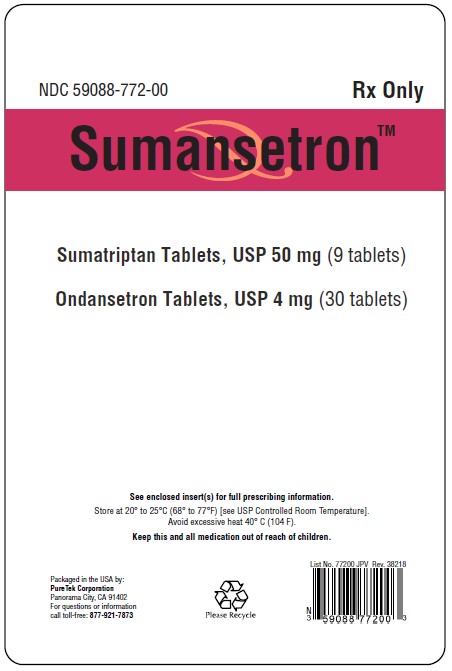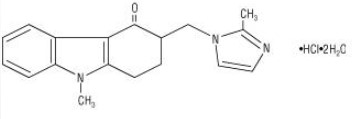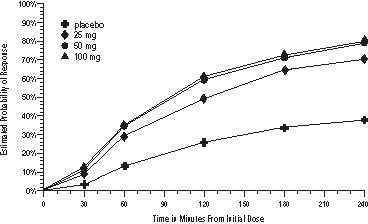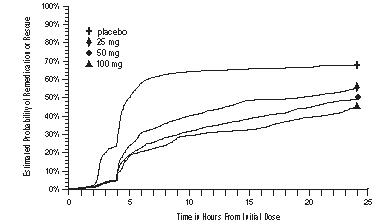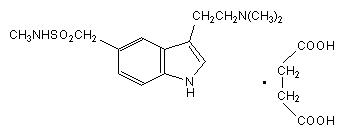 DRUG LABEL: Sumansetron
NDC: 59088-772 | Form: KIT | Route: ORAL
Manufacturer: PureTek Corporation
Category: prescription | Type: HUMAN PRESCRIPTION DRUG LABEL
Date: 20230111

ACTIVE INGREDIENTS: SUMATRIPTAN SUCCINATE 50 mg/1 1; ONDANSETRON HYDROCHLORIDE 4 mg/1 1
INACTIVE INGREDIENTS: CROSCARMELLOSE SODIUM; ANHYDROUS LACTOSE; LACTOSE MONOHYDRATE; MAGNESIUM STEARATE; MANNITOL; CELLULOSE, MICROCRYSTALLINE; TALC; TITANIUM DIOXIDE; TRIACETIN; MAGNESIUM STEARATE; LACTOSE MONOHYDRATE; TITANIUM DIOXIDE; TRIACETIN; STARCH, CORN; CROSCARMELLOSE SODIUM; HYPROMELLOSES; CELLULOSE, MICROCRYSTALLINE

HIGHLIGHTS OF PRESCRIBING INFORMATION

Sumansetron
These highlights do not include all the information needed to use ONDANSETRON TABLETS, USP safely and effectively. See full prescribing information for ONDANSETRON TABLETS, USP.
ONDANSETRON tablets USP, for oral use
Initial U.S. Approval: 1991

1 INDICATIONS AND USAGE

Ondansetron tablets are a 5-HT3 receptor antagonist indicated for the prevention of:
• nausea and vomiting associated with highly emetogenic cancer chemotherapy, including cisplatin ≥50 mg/m^2. (1)
• nausea and vomiting associated with initial and repeat courses of moderately emetogenic cancer chemotherapy. (1)
• nausea and vomiting associated with radiotherapy in patients receiving either total body irradiation, single high-dose fraction to the abdomen, or daily fractions to the abdomen. (1)
• postoperative nausea and/or vomiting. (1)

2 DOSAGE AND ADMINISTRATION

• See full prescribing information for the recommended dosage in adults and pediatrics (2)
• Patients with severe hepatic impairment: do not exceed a total daily dose of 8 mg (2.2, 8.6)

3 DOSAGE FORMS AND STRENGTHS

• Tablets: 4 mg and 8 mg (3)

4 CONTRAINDICATIONS

• Patients known to have hypersensitivity (e.g., anaphylaxis) to ondansetron or any components of the formulation. (4)
• Concomitant use of apomorphine. (4)

5 WARNINGS AND PRECAUTIONS

- Hypersensitivity reactions including anaphylaxis and bronchospasm: Discontinue ondansetron tablets if suspected. Monitor and treat promptly per standard of care until signs and symptoms resolve (5.1)
- QT interval prolongation and Torsade de Pointes: Avoid in patients with congenital long QT syndrome; monitor with electrocardiograms (ECGs) if concomitant electrolyte abnormalities, cardiac failure or arrhythmias, or use of other QT prolonging drugs. (5.2)
- Serotonin syndrome: Reported with 5-HT3 receptor antagonists alone but particularly with concomitant use of serotonergic drugs. If such symptoms occur, discontinue ondansetron tablets and initiate supportive treatment. If concomitant use of ondansetron tablets with other serotonergic drugs is clinically warranted, patients should be made aware of a potential increased risk for serotonin syndrome. (5.3)
- Masking of progressive ileus and/or gastric distention following abdominal surgery or chemotherapy-induced nausea and vomiting: Monitor for decreased bowel activity, particularly in patients with risk factors for gastrointestinal obstruction. (5.4)

6 ADVERSE REACTIONS

The most common adverse reactions in adults for the:
• prevention of chemotherapy-induced (greater than or equal to 5%) are: headache, malaise/fatigue, constipation, diarrhea. (6.1)
• prevention of radiation-induced nausea and vomiting (greater than or equal to 2%) are: headache, constipation, and diarrhea. (6.1)
• prevention of postoperative nausea and vomiting (greater than or equal to 9%) are: headache and hypoxia. (6.1)
To report SUSPECTED ADVERSE REACTIONS, contact Actavis Pharma Inc., at 1-800-432-8534 or FDA at 1-800-FDA-1088 or www.fda.gov/medwatch.

FULL PRESCRIBING INFORMATION

DESCRIPTION

Sumatriptan tablets USP contain sumatriptan (as the succinate), a selective 5-hydroxytryptamine1 receptor subtype agonist. Sumatriptan succinate USP is chemically designated as 3-[2- (dimethylamino) ethyl]-N-methyl-indole-5-methanesulfonamide succinate (1:1), and it has the following structure:

The molecular formula is C14H21N3O2S•C4H6O4, representing a molecular weight of 413.5. Sumatriptan succinate USP is a white to off-white powder that is readily soluble in water and in saline. Each sumatriptan tablet USP for oral administration contains 35, 70, or 140 mg of sumatriptan succinate USP equivalent to 25, 50, or 100 mg of sumatriptan, respectively. Each tablet also contains the inactive ingredients croscarmellose sodium, lactose anhydrous, lactose monohydrate, magnesium stearate, mannitol, microcrystalline cellulose, talc, titanium dioxide and triacetin.

CLINICAL PHARMACOLOGY

Mechanism of Action

Sumatriptan is an agonist for a vascular 5-hydroxytryptamine1 receptor subtype (probably a member of the 5-HT1D family) having only a weak affinity for 5-HT1A, 5-HT5A, and 5-HT7 receptors and no significant affinity (as measured using standard radioligand binding assays) or pharmacological activity at 5-HT2, 5-HT3, or 5-HT4 receptor subtypes or at alpha1-, alpha2-, or beta-adrenergic; dopamine1; dopamine2; muscarinic; or benzodiazepine receptors.

The vascular 5-HT1 receptor subtype that sumatriptan activates is present on cranial arteries in both dog and primate, on the human basilar artery, and in the vasculature of human dura mater and mediates vasoconstriction. This action in humans correlates with the relief of migraine headache. In addition to causing vasoconstriction, experimental data from animal studies show that sumatriptan also activates 5-HT1 receptors on peripheral terminals of the trigeminal nerve innervating cranial blood vessels. Such an action may also contribute to the antimigrainous effect of sumatriptan in humans.

In the anesthetized dog, sumatriptan selectively reduces the carotid arterial blood flow with little or no effect on arterial blood pressure or total peripheral resistance. In the cat, sumatriptan selectively constricts the carotid arteriovenous anastomoses while having little effect on blood flow or resistance in cerebral or extracerebral tissues.

Pharmacokinetics

The mean maximum concentration following oral dosing with 25 mg is 18 ng/mL (range: 7 to 47 ng/mL) and 51 ng/mL (range: 28 to 100 ng/mL) following oral dosing with 100 mg of sumatriptan. This compares with a Cmax of 5 and 16 ng/mL following dosing with a 5 and 20 mg intranasal dose, respectively. The mean Cmax following a 6 mg subcutaneous injection is 71 ng/mL (range: 49 to 110 ng/mL). The bioavailability is approximately 15%, primarily due to presystemic metabolism and partly due to incomplete absorption. The Cmax is similar during a migraine attack and during a migraine-free period, but the tmax is slightly later during the attack, approximately 2.5 hours compared to 2.0 hours. When given as a single dose, sumatriptan displays dose proportionality in its extent of absorption (area under the curve [AUC]) over the dose range of 25 to 200 mg, but the Cmax after 100 mg is approximately 25% less than expected (based on the 25 mg dose).

A food effect study involving administration of sumatriptan tablets 100 mg to healthy volunteers under fasting conditions and with a high-fat meal indicated that the Cmax and AUC were increased by 15% and 12 %, respectively, when administered in the fed state.

Plasma protein binding is low (14% to 21%). The effect of sumatriptan on the protein binding of other drugs has not been evaluated, but would be expected to be minor, given the low rate of protein binding. The apparent volume of distribution is 2.4 L/kg.

The elimination half-life of sumatriptan is approximately 2.5 hours. Radiolabeled^14C-sumatriptan administered orally is largely renally excreted (about 60%) with about 40% found in the feces. Most of the radiolabeled compound excreted in the urine is the major metabolite, indole acetic acid (IAA), which is inactive, or the IAA glucuronide. Only 3% of the dose can be recovered as unchanged sumatriptan.

In vitro studies with human microsomes suggest that sumatriptan is metabolized by monoamine oxidase (MAO), predominantly the A isoenzyme, and inhibitors of that enzyme may alter sumatriptan pharmacokinetics to increase systemic exposure. No significant effect was seen with an MAO-B inhibitor (see CONTRAINDICATIONS, WARNINGS, and PRECAUTIONS: Drug Interactions).

Special Populations

Renal Impairment

Renal Impairment: The effect of renal impairment on the pharmacokinetics of sumatriptan has not been examined, but little clinical effect would be expected as sumatriptan is largely metabolized to an inactive substance.

Hepatic Impairment

The liver plays an important role in the presystemic clearance of orally administered sumatriptan. Accordingly, the bioavailability of sumatriptan following oral administration may be markedly increased in patients with liver disease. In 1 small study of hepatically impaired patients (N = 8) matched for sex, age, and weight with healthy subjects, the hepatically impaired patients had an approximately 70% increase in AUC and Cmax and a tmax 40 minutes earlier compared to the healthy subjects (see DOSAGE AND ADMINISTRATION).

Age

The pharmacokinetics of oral sumatriptan in the elderly (mean age, 72 years; 2 males and 4 females) and in patients with migraine (mean age, 38 years; 25 males and 155 females) were similar to that in healthy male subjects (mean age, 30 years) (see PRECAUTIONS: Geriatric Use).

Gender

In a study comparing females to males, no pharmacokinetic differences were observed between genders for AUC, Cmax, tmax, and half-life.

Race

The systemic clearance and Cmax of sumatriptan were similar in black (N = 34) and Caucasian (N = 38) healthy male subjects.

Drug Interactions

Monoamine Oxidase Inhibitors (MAO)

Treatment with MAO-A inhibitors generally leads to an increase of sumatriptan plasma levels (see CONTRAINDICATIONS and PRECAUTIONS).

Due to gut and hepatic metabolic first-pass effects, the increase of systemic exposure after coadministration of an MAO-A inhibitor with oral sumatriptan is greater than after coadministration of the monoamine oxidase inhibitors (MAOI) with subcutaneous sumatriptan. In a study of 14 healthy females, pretreatment with an MAO-A inhibitor decreased the clearance of subcutaneous sumatriptan. Under the conditions of this experiment, the result was a 2-fold increase in the area under the sumatriptan plasma concentration x time curve (AUC), corresponding to a 40% increase in elimination half-life. This interaction was not evident with an MAO-B inhibitor.

A small study evaluating the effect of pretreatment with an MAO-A inhibitor on the bioavailability from a 25 mg oral sumatriptan tablet resulted in an approximately 7-fold increase in systemic exposure.

Alcohol

Alcohol consumed 30 minutes prior to sumatriptan ingestion had no effect on the pharmacokinetics of sumatriptan.

CLINICAL STUDIES

The efficacy of sumatriptan tablets in the acute treatment of migraine headaches was demonstrated in 3, randomized, double-blind, placebo-controlled studies. Patients enrolled in these 3 studies were predominately female (87%) and Caucasian (97%), with a mean age of 40 years (range, 18 to 65 years). Patients were instructed to treat a moderate to severe headache. Headache response, defined as a reduction in headache severity from moderate or severe pain to mild or no pain, was assessed up to 4 hours after dosing. Associated symptoms such as nausea, photophobia, and phonophobia were also assessed. Maintenance of response was assessed for up to 24 hours postdose. A second dose of sumatriptane tablets or other medication was allowed 4 to 24 hours after the initial treatment for recurrent headache. Acetaminophen was offered to patients in Studies 2 and 3 beginning at 2 hours after initial treatment if the migraine pain had not improved or worsened. Additional medications were allowed 4 to 24 hours after the initial treatment for recurrent headache or as rescue in all 3 studies. The frequency and time to use of these additional treatments were also determined. In all studies, doses of 25, 50, and 100 mg were compared to placebo in the treatment of migraine attacks. In 1 study, doses of 25, 50, and 100 mg were also compared to each other.

In all 3 trials, the percentage of patients achieving headache response 2 and 4 hours after treatment was significantly greater among patients receiving sumatriptan tablets at all doses compared to those who received placebo. In 1 of the 3 studies, there was a statistically significant greater percentage of patients with headache response at 2 and 4 hours in the 50 or 100 mg group when compared to the 25 mg dose groups. There were no statistically significant differences between the 50 and 100 mg dose groups in any study. The results from the 3 controlled clinical trials are summarized in Table 1.

Comparisons of drug performance based upon results obtained in different clinical trials are never reliable. Because studies are conducted at different times, with different samples of patients, by different investigators, employing different criteria and/or different interpretations of the same criteria, under different conditions (dose, dosing regimen, etc.), quantitative estimates of treatment response and the timing of response may be expected to vary considerably from study to study.

Table 1. Percentage of Patients With Headache Response (No or Mild Pain) 2 and 4 Hours Following Treatment
 | Placebo; 2 hr 4 hr | Sumatriptan Tablets; 25 mg; 2 hr 4 hr | Sumatriptan Tablets; 50 mg; 2 hr 4 hr | Sumatriptan Tablets; 100 mg; 2 hr 4 hr
Study 1 | 27% 38% | 52%a 67%a | 61%ab %ab | 62%ab 79%ab
 | (N = 94) | (N = 298) | (N = 296) | (N = 296)
Study 2 | 26% 38% | 52%a 70%a | 50%a 68%a | 56%a 71%a
 | (N = 65) | (N = 66) | (N = 62) | (N = 66)
Study 3 | 17% 19% | 52%a 65%a | 54%a 72%a | 57%a 78%a
 | (N = 47) | (N = 48) | (N = 46) | (N = 46)

ap<0.05 in comparison with placebo.

bp<0.05 in comparison with 25 mg.

The estimated probability of achieving an initial headache response over the 4 hours following treatment is depicted in Figure 1.

a The figure shows the probability over time of obtaining headache response (no or mild pain) following treatment with sumatriptan. The averages displayed are based on pooled data from the 3 clinical controlled trials providing evidence of efficacy. Kaplan-Meier plot with patients not achieving response and/or taking rescue within 240 minutes censored to 240 minutes.

For patients with migraine-associated nausea, photophobia, and/or phonophobia at baseline, there was a lower incidence of these symptoms at 2 hours (Study 1) and at 4 hours (Studies 1, 2, and 3) following administration of sumatriptan tablets compared to placebo.

As early as 2 hours in Studies 2 and 3 or 4 hours in Study 1, through 24 hours following the initial dose of study treatment, patients were allowed to use additional treatment for pain relief in the form of a second dose of study treatment or other medication. The estimated probability of patients taking a second dose or other medication for migraine over the 24 hours following the initial dose of study treatment is summarized in Figure 2.

aKaplan-Meier plot based on data obtained in the 3 clinical controlled trials providing evidence of efficacy with patients not using additional treatments censored to 24 hours. Plot also includes patients who had no response to the initial dose. No remedication was allowed within 2 hours postdose.

There is evidence that doses above 50 mg do not provide a greater effect than 50 mg. There was no evidence to suggest that treatment with sumatriptan was associated with an increase in the severity of recurrent headaches. The efficacy of sumatriptan tablets was unaffected by presence of aura; duration of headache prior to treatment; gender, age, or weight of the patient; relationship to menses; or concomitant use of common migraine prophylactic drugs (e.g., beta-blockers, calcium channel blockers, tricyclic antidepressants). There were insufficient data to assess the impact of race on efficacy.

INDICATIONS AND USAGE

Sumatriptan tablets are indicated for the acute treatment of migraine attacks with or without aura in adults.

Sumatriptan tablets are not intended for the prophylactic therapy of migraine or for use in the management of hemiplegic or basilar migraine (see CONTRAINDICATIONS). Safety and effectiveness of sumatriptan tablets have not been established for cluster headache, which is present in an older, predominantly male population.

CONTRAINDICATIONS

Sumatriptan tablets should not be given to patients with history, symptoms, or signs of ischemic cardiac, cerebrovascular, or peripheral vascular syndromes. In addition, patients with other significant underlying cardiovascular diseases should not receive sumatriptane tablets. Ischemic cardiac syndromes include, but are not limited to, angina pectoris of any type (e.g., stable angina of effort, vasospastic forms of angina such as the Prinzmetal variant), all forms of myocardial infarction, and silent myocardial ischemia.

Cerebrovascular syndromes include, but are not limited to, strokes of any type as well as transient ischemic attacks. Peripheral vascular disease includes, but is not limited to, ischemic bowel disease (see WARNINGS).

Because sumatriptan tablets may increase blood pressure, they should not be given to patients with uncontrolled hypertension.

Concurrent administration of MAO-A inhibitors or use within 2 weeks of discontinuation of MAO-A inhibitor therapy is contraindicated (see CLINICAL PHARMACOLOGY: Drug Interactions and PRECAUTIONS: Drug Interactions).

Sumatriptan tablets should not be administered to patients with hemiplegic or basilar migraine.

Sumatriptan tablets and any ergotamine-containing or ergot-type medication (like dihydroergotamine or methysergide) should not be used within 24 hours of each other, nor should sumatriptan and another 5-HT1 agonist.

Sumatriptan tablets are contraindicated in patients with hypersensitivity to sumatriptan or any of their components.

Sumatriptan tablets are contraindicated in patients with severe hepatic impairment.

WARNINGS

Sumatriptan tablets should only be used where a clear diagnosis of migraine headache has been established.

Risk of Myocardial Ischemia and/or Infarction and Other Adverse Cardiac Events

Sumatriptan should not be given to patients with documented ischemic or vasospastic coronary artery disease (CAD) (see CONTRAINDICATIONS). It is strongly recommended that sumatriptan not be given to patients in whom unrecognized CAD is predicted by the presence of risk factors (e.g., hypertension, hypercholesterolemia, smoker, obesity, diabetes, strong family history of CAD, female with surgical or physiological menopause, or male over 40 years of age) unless a cardiovascular evaluation provides satisfactory clinical evidence that the patient is reasonably free of coronary artery and ischemic myocardial disease or other significant underlying cardiovascular disease. The sensitivity of cardiac diagnostic procedures to detect cardiovascular disease or predisposition to coronary artery vasospasm is modest, at best. If, during the cardiovascular evaluation, the patient’s medical history or electrocardiographic investigations reveal findings indicative of, or consistent with, coronary artery vasospasm or myocardial ischemia, sumatriptan should not be administered (see CONTRAINDICATIONS).

For patients with risk factors predictive of CAD, who are determined to have a satisfactory cardiovascular evaluation, it is strongly recommended that administration of the first dose of sumatriptan tablets take place in the setting of a physician’s office or similar medically staffed and equipped facility unless the patient has previously received sumatriptan. Because cardiac ischemia can occur in the absence of clinical symptoms, consideration should be given to obtaining on the first occasion of use an electrocardiogram (ECG) during the interval immediately following sumatriptan tablets, in these patients with risk factors.

It is recommended that patients who are intermittent long-term users of sumatriptan and who have or acquire risk factors predictive of CAD, as described above, undergo periodic interval cardiovascular evaluation as they continue to use sumatriptan.

The systematic approach described above is intended to reduce the likelihood that patients with unrecognized cardiovascular disease will be inadvertently exposed to sumatriptan.

Drug-Associated Cardiac Events and Fatalities

Serious adverse cardiac events, including acute myocardial infarction, life-threatening disturbances of cardiac rhythm, and death have been reported within a few hours following the administration of sumatriptan succinate injection or sumatriptan tablets. Considering the extent of use of sumatriptan in patients with migraine, the incidence of these events is extremely low.

The fact that sumatriptan can cause coronary vasospasm, that some of these events have occurred in patients with no prior cardiac disease history and with documented absence of CAD, and the close proximity of the events to sumatriptan use support the conclusion that some of these cases were caused by the drug. In many cases, however, where there has been known underlying coronary artery disease, the relationship is uncertain.

Premarketing Experience With Sumatriptan

Of 6,348 patients with migraine who participated in premarketing controlled and uncontrolled clinical trials of oral sumatriptan, 2 experienced clinical adverse events shortly after receiving oral sumatriptan that may have reflected coronary vasospasm. Neither of these adverse events was associated with a serious clinical outcome.

Among the more than 1,900 patients with migraine who participated in premarketing controlled clinical trials of subcutaneous sumatriptan, there were 8 patients who sustained clinical events during or shortly after receiving sumatriptan that may have reflected coronary artery vasospasm. Six of these 8 patients had ECG changes consistent with transient ischemia, but without accompanying clinical symptoms or signs. Of these 8 patients, 4 had either findings suggestive of CAD or risk factors predictive of CAD prior to study enrollment.

Among approximately 4,000 patients with migraine who participated in premarketing controlled and uncontrolled clinical trials of sumatriptan nasal spray, 1 patient experienced an asymptomatic subendocardial infarction possibly subsequent to a coronary vasospastic event.

Postmarketing Experience With Sumatriptan

Serious cardiovascular events, some resulting in death, have been reported in association with the use of sumatriptan succinate injection or sumatriptan tablets. The uncontrolled nature of postmarketing surveillance, however, makes it impossible to determine definitively the proportion of the reported cases that were actually caused by sumatriptan or to reliably assess causation in individual cases. On clinical grounds, the longer the latency between the administration of sumatriptan and the onset of the clinical event, the less likely the association is to be causative. Accordingly, interest has focused on events beginning within 1 hour of the administration of sumatriptan.

Cardiac events that have been observed to have onset within 1 hour of sumatriptan administration include: coronary artery vasospasm, transient ischemia, myocardial infarction, ventricular tachycardia and ventricular fibrillation, cardiac arrest, and death.

Some of these events occurred in patients who had no findings of CAD and appear to represent consequences of coronary artery vasospasm. However, among domestic reports of serious cardiac events within 1 hour of sumatriptan administration, almost all of the patients had risk factors predictive of CAD and the presence of significant underlying

Drug-Associated Cerebrovascular Events and Fatalities

Cerebral hemorrhage, subarachnoid hemorrhage, stroke, and other cerebrovascular events have been reported in patients treated with oral or subcutaneous sumatriptan, and some have resulted in fatalities. The relationship of sumatriptan to these events is uncertain. In a number of cases, it appears possible that the cerebrovascular events were primary, sumatriptan having been administered in the incorrect belief that the symptoms experienced were a consequence of migraine when they were not. As with other acute migraine therapies, before treating headaches in patients not previously diagnosed as migraineurs, and in migraineurs who present with atypical symptoms, care should be taken to exclude other potentially serious neurological conditions. It should also be noted that patients with migraine may be at increased risk of certain cerebrovascular events (e.g., cerebrovascular accident, transient ischemic attack).

Other Vasospasm-Related Events

Sumatriptan may cause vasospastic reactions other than coronary artery vasospasm. Both peripheral vascular ischemia and colonic ischemia with abdominal pain and bloody diarrhea have been reported. Very rare reports of transient and permanent blindness and significant partial vision loss have been reported with the use of sumatriptan. Visual disorders may also be part of a migraine attack.

Serotonin Syndrome

Serotonin syndrome may occur with triptans, including Sumatriptan, particularly during combined use with selective serotonin reuptake inhibitors (SSRIs) or serotonin norepinephrine reuptake inhibitors (SNRIs).Serotonin synd rome symptoms may include mental status changes (e.g., agitation, hallucinations, coma), autonomic instability (e.g ., tachycardia, labile blood pressure, hyperthermia), neuromuscular aberrations (e.g., hyperr eflexia, incoordination), and/or gastrointestinal symptoms (e.g., nausea, vomiting, diarrhea). The on set of symptoms can occur within minutes to hours of receiving a new or a greater dose of a serotonergic medication. Treatment with Sumatriptan treatment should be discontinued if serotonin syndrome is suspected.

Increase in Blood Pressure

Significant elevation in blood pressure, including hypertensive crisis, has been reported on rare occasions in patients with and without a history of hypertension. Sumatriptan is contraindicated in patients with uncontrolled hypertension (see CONTRAINDICATIONS). Sumatriptan should be administered with caution to patients with controlled hypertension as transient increases in blood pressure and peripheral vascular resistance have been observed in a small proportion of patients.

Concomitant Drug Use

In patients taking MAO-A inhibitors, sumatriptan plasma levels attained after treatment with recommended doses are 7-fold higher following oral administration than those obtained under other conditions. Accordingly, the coadministration of sumatriptan tablets and an MAO-A inhibitor is contraindicated (see CLINICAL PHARMACOLOGY and CONTRAINDICATIONS).

Hypersensitivity

Hypersensitivity (anaphylaxis/anaphylactoid) reactions have occurred on rare occasions in patients receiving sumatriptan. Such reactions can be life threatening or fatal. In general, hypersensitivity reactions to drugs are more likely to occur in individuals with a history of sensitivity to multiple allergens (see CONTRAINDICATIONS).

PRECAUTIONS

General

Chest discomfort and jaw or neck tightness have been reported following use of sumatriptan tablets and have also been reported infrequently following administration of sumatriptan succinate Nasal Spray. Chest, jaw, or neck tightness is relatively common after administration of sumatriptan succinate injection. Only rarely have these symptoms been associated with ischemic ECG changes. However, because sumatriptan may cause coronary artery vasospasm, patients who experience signs or symptoms suggestive of angina following sumatriptan should be evaluated for the presence of CAD or a predisposition to Prinzmetal variant angina before receiving additional doses of sumatriptan, and should be monitored electrocardiographically if dosing is resumed and similar symptoms recur. Similarly, patients who experience other symptoms or signs suggestive of decreased arterial flow, such as ischemic bowel syndrome or Raynaud syndrome following sumatriptan should be evaluated for atherosclerosis or predisposition to vasospasm (see WARNINGS).

Sumatriptan should also be administered with caution to patients with diseases that may alter the absorption, metabolism, or excretion of drugs, such as impaired hepatic or renal function.

There have been rare reports of seizure following administration of sumatriptan. Sumatriptan should be used with caution in patients with a history of epilepsy or conditions associated with a lowered seizure threshold.

Care should be taken to exclude other potentially serious neurologic conditions before treating headache in patients not previously diagnosed with migraine headache or who experience a headache that is atypical for them. There have been rare reports where patients received sumatriptan for severe headaches that were subsequently shown to have been secondary to an evolving neurologic lesion (see WARNINGS).

For a given attack, if a patient does not respond to the first dose of sumatriptan, the diagnosis of migraine should be reconsidered before administration of a second dose.

Overuse:

Overuse of acute migraine drugs (e.g., ergotamine, triptans, opioids, or a combination of drugs for 10 or more days per month) may lead to exacerbation of headache (medication overuse headache). Medication overuse headache may present as migraine-like daily headaches, or as a marked increase in frequency of migraine attacks. Detoxification of patients, including withdrawal of the overused drugs, and treatment of withdrawal symptoms (which often includes a transient worsening of headache) may be necessary. Migraine patients should be informed about the risks of medication overuse, and encouraged to record headache frequency and drug use.

Information for Patients

See PATIENTINFORMATION at the end of this labeling for the text of the separate leaflet provided for patients.

Patients should be cautioned about the risk of serotonin syndrome with the use of sumatriptan or other triptans, especially during combined use with SSRIs or SNRIs.

Laboratory Tests

No specific laboratory tests are recommended for monitoring patients prior to and/or after treatment with sumatriptan.

Drug Interactions

Selective Serotonin Reuptake Inhibitors/Serotonin Norepinephrine Reuptake Inhibitors and Serotonin Syndrome:

Cases of life‑threatening serotonin syndrome have been reported during combined use of SSRIs or SNRIs and triptans (see WARNINGS).

Ergot-containing drugs have been reported to cause prolonged vasospastic reactions. Because there is a theoretical basis that these effects may be additive, use of ergotamine-containing or ergot-type medications (like dihydroergotamine or methysergide) and sumatriptan within 24 hours of each other should be avoided (see CONTRAINDICATIONS).

Monoamine Oxidase-A Inhibitors

MAO-A inhibitors reduce sumatriptan clearance, significantly increasing systemic exposure. Therefore, the use of sumatriptan tablets in patients receiving MAO-A inhibitors is contraindicated (see CLINICALPHARMACOLOGY and CONTRAINDICATIONS).

Drug/Laboratory Test Interactions

Sumatriptan tablets are not known to interfere with commonly employed clinical laboratory tests.

Carcinogenesis, Mutagenesis, Impairment of Fertility

Carcinogenesis:

In carcinogenicity studies, rats and mice were given sumatriptan by oral gavage (rats: 104 weeks) or drinking water (mice: 78 weeks). Average exposures achieved in mice receiving the highest dose (target dose of 160 mg/kg/day) were approximately 40 times the exposure attained in humans after the maximum recommended single oral dose of 100 mg. The highest dose administered to rats (160 mg/kg/day, reduced from 360 mg/kg/day during week 21) was approximately 15 times the maximum recommended single human oral dose of 100 mg on a mg/m^2 basis. There was no evidence of an increase in tumors in either species related to sumatriptan administration.

Mutagenesis

Sumatriptan was not mutagenic in the presence or absence of metabolic activation when tested in 2 gene mutation assays (the Ames test and the in vitro mammalian Chinese hamster V79/HGPRT assay). In 2 cytogenetics assays (the in vitro human lymphocyte assay and the in vivo rat micronucleus assay) sumatriptan was not associated with clastogenic activity.

Impairment of Fertility

In a study in which male and female rats were dosed daily with oral sumatriptan prior to and throughout the mating period, there was a treatment-related decrease in fertility secondary to a decrease in mating in animals treated with 50 and 500 mg/kg/day. The highest no-effect dose for this finding was 5 mg/kg/day, or approximately one half of the maximum recommended single human oral dose of 100 mg on a mg/m^2 basis. It is not clear whether the problem is associated with treatment of the males or females or both combined. In a similar study by the subcutaneous route there was no evidence of impaired fertility at 60 mg/kg/day, the maximum dose tested, which is equivalent to approximately 6 times the maximum recommended single human oral dose of 100 mg on a mg/m^2 basis.

Pregnancy

Teratogenic Effects: Pregnancy Category C. In reproductive toxicity studies in rats and rabbits, oral treatment with sumatriptan was associated with embryolethality, fetal abnormalities, and pup mortality. When administered by the intravenous route to rabbits, sumatriptan has been shown to be embryolethal. There are no adequate and well-controlled studies in pregnant women. Therefore, sumatriptan should be used during pregnancy only if the potential benefit justifies the potential risk to the fetus. In assessing this information, the following findings should be considered.

Embryolethality

When given orally or intravenously to pregnant rabbits daily throughout the period of organogenesis, sumatriptan caused embryolethality at doses at or close to those producing maternal toxicity. In the oral studies this dose was 100 mg/kg/day, and in the intravenous studies this dose was 2 mg/kg/day. The mechanism of the embryolethality is not known. The highest no-effect dose for embryolethality by the oral route was 50 mg/kg/day, which is approximately 9 times the maximum single recommended human oral dose of 100 mg on a mg/m^2 basis. By the intravenous route, the highest no-effect dose was 0.75 mg/kg/day, or approximately one tenth of the maximum single recommended human oral dose of 100 mg on a mg/m^2 basis.

The intravenous administration of sumatriptan to pregnant rats throughout organogenesis at 12.5 mg/kg/day, the maximum dose tested, did not cause embryolethality. This dose is equivalent to the maximum single recommended human oral dose of 100 mg on a mg/m^2 basis. Additionally, in a study in rats given subcutaneous sumatriptan daily prior to and throughout pregnancy at 60 mg/kg/day, the maximum dose tested, there was no evidence of increased embryo/fetal lethality. This dose is equivalent to approximately 6 times the maximum recommended single human oral dose of 100 mg on a mg/m^2 basis.

Teratogenicity

Oral treatment of pregnant rats with sumatriptan during the period of organogenesis resulted in an increased incidence of blood vessel abnormalities (cervicothoracic and umbilical) at doses of approximately 250 mg/kg/day or higher. The highest no-effect dose was approximately 60 mg/kg/day, which is approximately 6 times the maximum single recommended human oral dose of 100 mg on a mg/m^2 basis. Oral treatment of pregnant rabbits with sumatriptan during the period of organogenesis resulted in an increased incidence of cervicothoracic vascular and skeletal abnormalities. The highest no-effect dose for these effects was 15 mg/kg/day, or approximately 3 times the maximum single recommended human oral dose of 100 mg on a mg/m^2 basis.

A study in which rats were dosed daily with oral sumatriptan prior to and throughout gestation demonstrated embryo/fetal toxicity (decreased body weight, decreased ossification, increased incidence of rib variations) and an increased incidence of a syndrome of malformations (short tail/short body and vertebral disorganization) at 500 mg/kg/day. The highest no-effect dose was 50 mg/kg/day, or approximately 5 times the maximum single recommended human oral dose of 100 mg on a mg/m^2 basis. In a study in rats dosed daily with subcutaneous sumatriptan prior to and throughout pregnancy, at a dose of 60 mg/kg/day, the maximum dose tested, there was no evidence of teratogenicity. This dose is equivalent to approximately 6 times the maximum recommended single human oral dose of 100 mg on a mg/m^2 basis.

Pup Deaths

Oral treatment of pregnant rats with sumatriptan during the period of organogenesis resulted in a decrease in pup survival between birth and postnatal day 4 at doses of approximately 250 mg/kg/day or higher. The highest no-effect dose for this effect was approximately 60 mg/kg/day, or 6 times the maximum single recommended human oral dose of 100 mg on a mg/m^2 basis.

Oral treatment of pregnant rats with sumatriptan from gestational day 17 through postnatal day 21 demonstrated a decrease in pup survival measured at postnatal days 2, 4, and 20 at the dose of 1,000 mg/kg/day. The highest no-effect dose for this finding was 100 mg/kg/day, approximately 10 times the maximum single recommended human oral dose of 100 mg on a mg/m^2 basis. In a similar study in rats by the subcutaneous route there was no increase in pup death at 81 mg/kg/day, the highest dose tested, which is equivalent to 8 times the maximum single recommended human oral dose of 100 mg on a mg/m^2 basis.

Nursing Mothers

Sumatriptan is excreted in human breast milk following subcutaneous administration. Infant exposure to sumatriptan can be minimized by avoiding breastfeeding for 12 hours after treatment with sumatriptan tablets.

Pediatric Use

Safety and effectiveness of sumatriptan tablets in pediatric patients have not been established.

Completed placebo-controlled clinical trials evaluating oral sumatriptan (25 to 100 mg) in pediatric patients aged 12 to 17 years enrolled a total of 701 adolescent migraineurs. These studies did not establish the efficacy of oral sumatriptan compared to placebo in the treatment of migraine in adolescents. Adverse events observed in these clinical trials were similar in nature to those reported in clinical trials in adults. The frequency of all adverse events in theses patients appeared to be both dose- and age-dependent, with younger patients reporting events more commonly than older adolescents. Post-marketing experience includes a limited number of reports that describe pediatric patients who have experienced adverse events, some clinically serious, after use of subcutaneous sumatriptan and/or oral sumatriptan. These reports include events similar in nature to those reported rarely in adults. A myocardial infarct has been reported in a 14-year-old male following the use of oral sumatriptan; clinical signs occurred within 1 day of drug administration. Since clinical data to determine the frequency of serious adverse events in pediatric patients who might receive injectable, oral, or intranasal sumatriptan are not presently available, the use of sumatriptan in patients aged younger than 18 years is not recommended.

Geriatric Use

The use of sumatriptan in elderly patients is not recommended because elderly patients are more likely to have decreased hepatic function, they are at higher risk for CAD, and blood pressure increases may be more pronounced in the elderly (see WARNINGS).

ADVERSE REACTIONS

Serious cardiac events, including some that have been fatal, have occurred following the use of sumatriptan succinate injection or tablets. These events are extremely rare and most have been reported in patients with risk factors predictive of CAD. Events reported have included coronary artery vasospasm, transient myocardial ischemia, myocardial infarction, ventricular tachycardia, and ventricular fibrillation (see CONTRAINDICATIONS, WARNINGS, and PRECAUTIONS) .

Significant hypertensive episodes, including hypertensive crises, have been reported on rare occasions in patients with or without a history of hypertension (see WARNINGS).

Incidence in Controlled Clinical Trials

Table 2 lists adverse events that occurred in placebo-controlled clinical trials in patients who took at least 1 dose of study drug. Only events that occurred at a frequency of 2% or more in any group treated with sumatriptan tablets and were more frequent in that group than in the placebo group are included in Table 2. The events cited reflect experience gained under closely monitored conditions of clinical trials in a highly selected patient population. In actual clinical practice or in other clinical trials, these frequency estimates may not apply, as the conditions of use, reporting behavior, and the kinds of patients treated may differ.

Table 2. Treatment Emergent Adverse Events Reported by at Least 2% of Patients in Controlled Migraine Trialsa
Adverse Event Type | Percent of Patients Reporting
Adverse Event Type | Placebo; (N = 309) | Sumatriptan; 25 mg; (N = 417) | Sumatriptan; 50 mg; (N = 771) | Sumatriptan; 100 mg; (N = 437)
Atypical sensations | 4% | 5% | 6% | 6%
Paresthesia (all types) | 2% | 3% | 5% | 3%
Sensation warm/cold | 2% | 3% | 2% | 3%
Pain and other pressure sensations | 4% | 6% | 6% | 8%
Chest - pain/tightness/pressure and/or heaviness | 1% | 1% | 2% | 2%
Neck/throat/jaw - pain/ tightness/pressure | <1% | <1% | 2% | 3%
Pain - location specified | 1% | 2% | 1% | 1%
Other - pressure/tightness/ heaviness | 2% | 1% | 1% | 3%
Neurological
Vertigo | <1% | <1% | <1% | 2%
Other
Malaise/fatigue | <1% | 2% | 2% | 3%

aEvents that occurred at a frequency of 2% or more in the group treated with sumatriptan tablets and that occurred more frequently in that group than the placebo group.

Other events that occurred in more than 1% of patients receiving sumatriptan tablets and at least as often on placebo included nausea and/or vomiting, migraine, headache, hyposalivation, dizziness, and drowsiness/sleepiness.

Sumatriptan tablets are generally well tolerated. Across all doses, most adverse reactions were mild and transient and did not lead to long-lasting effects. The incidence of adverse events in controlled clinical trials was not affected by gender or age of the patients. There were insufficient data to assess the impact of race on the incidence of adverse events.

Other Events Observed in Association With the Administration of Sumatriptan Tablets

In the paragraphs that follow, the frequencies of less commonly reported adverse clinical events are presented. Because the reports include events observed in open and uncontrolled studies, the role of sumatriptan tablets in their causation cannot be reliably determined. Furthermore, variability associated with adverse event reporting, the terminology used to describe adverse events, etc., limit the value of quantitative frequency estimates provided. Event frequencies are calculated as the number of patients who used sumatriptane tablets (25, 50, or 100 mg) and reported an event divided by the total number of patients (N = 6,348) exposed to sumatriptan tablets. All reported events are included except those already listed in the previous table, those too general to be informative, and those not reasonably associated with the use of the drug. Events are further classified within body system categories and enumerated in order of decreasing frequency using the following definitions: frequent adverse events are defined as those occurring in at least 1/100 patients, infrequent adverse events are those occurring in 1/100 to 1/1,000 patients, and rare adverse events are those occurring in fewer than 1/1,000 patients.

Atypical Sensations

Frequent were burning sensation and numbness. Infrequent was tight feeling in head. Rare were dysesthesia.

Cardiovascular

Frequent were palpitations, syncope, decreased blood pressure, and increased blood pressure. Infrequent were arrhythmia, changes in ECG, hypertension, hypotension, pallor, pulsating sensations, and tachycardia. Rare were angina, atherosclerosis, bradycardia, cerebral ischemia, cerebrovascular lesion, heart block, peripheral cyanosis, thrombosis, transient myocardial ischemia, and vasodilation.

Ear, Nose, and Throat

Frequent were sinusitis, tinnitus; allergic rhinitis; upper respiratory inflammation; ear, nose, and throat hemorrhage; external otitis; hearing loss; nasal inflammation; and sensitivity to noise. Infrequent were hearing disturbances and otalgia. Rare was feeling of fullness in the ear(s).

Endocrine and Metabolic

Infrequent was thirst. Rare were elevated thyrotropin stimulating hormone (TSH) levels; galactorrhea; hyperglycemia; hypoglycemia; hypothyroidism; polydipsia; weight gain; weight loss; endocrine cysts, lumps, and masses; and fluid disturbances.

Eye

Rare were disorders of sclera, mydriasis, blindness and low vision, visual disturbances, eye edema and swelling, eye irritation and itching, accommodation disorders, external ocular muscle disorders, eye hemorrhage, eye pain, and keratitis and conjunctivitis.

Gastrointestinal

Frequent were diarrhea and gastric symptoms. Infrequent were constipation, dysphagia, and gastroesophageal reflux. Rare were gastrointestinal bleeding, hematemesis, melena, peptic ulcer, gastrointestinal pain, dyspeptic symptoms, dental pain, feelings of gastrointestinal pressure, gastritis, gastroenteritis, hypersalivation, abdominal distention, oral itching and irritation, salivary gland swelling, and swallowing disorders.

Hematological Disorders

Rare was anemia.

Musculoskeletal

Frequent was myalgia. Infrequent was muscle cramps. Rare were tetany; muscle atrophy, weakness, and tiredness; arthralgia and articular rheumatitis; acquired musculoskeletal deformity; muscle stiffness, tightness, and rigidity; and musculoskeletal inflammation.

Neurological

Frequent were phonophobia and photophobia. Infrequent were confusion, depression, difficulty concentrating, disturbance of smell, dysarthria, euphoria, facial pain, heat sensitivity, incoordination, lacrimation, monoplegia, sleep disturbance, shivering, syncope, and tremor. Rare were aggressiveness, apathy, bradylogia, cluster headache, convulsions, decreased appetite, drug abuse, dystonic reaction, facial paralysis, hallucinations, hunger, hyperesthesia, hysteria, increased alertness, memory disturbance, neuralgia, paralysis, personality change, phobia, radiculopathy, rigidity, suicide, twitching, agitation, anxiety, depressive disorders, detachment, motor dysfunction, neurotic disorders, psychomotor disorders, taste disturbances, and raised intracranial pressure.

Respiratory

Frequent was dyspnea. Infrequent was asthma. Rare were hiccoughs, breathing disorders, cough, and bronchitis.

Skin

Frequent was sweating. Infrequent were erythema, pruritus, rash, and skin tenderness. Rare were dry/scaly skin, tightness of skin, wrinkling of skin, eczema, seborrheic dermatitis, and skin nodules.

Breasts

Infrequent was tenderness. Rare were nipple discharge; breast swelling; cysts, lumps, and masses of breasts; and primary malignant breast neoplasm.

Urogenital

Infrequent were dysmenorrhea, increased urination, and intermenstrual bleeding. Rare were abortion and hematuria, urinary frequency, bladder inflammation, micturition disorders, urethritis, urinary infections, menstruation symptoms, abnormal menstrual cycle, inflammation of fallopian tubes, and menstrual cycle symptoms.

Miscellaneous

Frequent was hypersensitivity. Infrequent were fever, fluid retention, and overdose. Rare were edema, hematoma, lymphadenopathy, speech disturbance, voice disturbances, contusions.

Other Events Observed in the Clinical Development of Sumatriptan

The following adverse events occurred in clinical trials with sumatriptan succinate injection and sumatriptan succinate nasal spray. Because the reports include events observed in open and uncontrolled studies, the role of sumatriptan in their causation cannot be reliably determined. All reported events are included except those already listed, those too general to be informative, and those not reasonably associated with the use of the drug.

Atypical Sensations

Feeling strange, prickling sensation, tingling, and hot sensation.

Cardiovascular

Abdominal aortic aneurysm, abnormal pulse, flushing, phlebitis, Raynaud syndrome, and various transient ECG changes (nonspecific ST or T wave changes, prolongation of PR or QTc intervals, sinus arrhythmia, nonsustained ventricular premature beats, isolated junctional ectopic beats, atrial ectopic beats, delayed activation of the right ventricle).

Chest Symptoms

Chest discomfort.

Endocrine and Metabolic

Dehydration.

Ear, Nose, and Throat

Disorder/discomfort nasal cavity and sinuses, ear infection, Meniere disease, and throat discomfort.

Eye

Vision alterations.

Gastrointestinal

Abdominal discomfort, colitis, disturbance of liver function tests, flatulence/eructation, gallstones, intestinal obstruction, pancreatitis, and retching.

Miscellaneous

Difficulty in walking, hypersensitivity to various agents, jaw discomfort, miscellaneous laboratory abnormalities, “serotonin agonist effect,” swelling of the extremities, and swelling of the face.

Mouth and Teeth

Disorder of mouth and tongue (e.g., burning of tongue, numbness of tongue, dry mouth).

Musculoskeletal

Arthritis, backache, intervertebral disc disorder, neck pain/stiffness, need to flex calf muscles, and various joint disturbances (pain, stiffness, swelling, ache).

Neurological

Bad/unusual taste, chills, diplegia, disturbance of emotions, sedation, globus hystericus, intoxication, myoclonia, neoplasm of pituitary, relaxation, sensation of lightness, simultaneous hot and cold sensations, stinging sensations, stress, tickling sensations, transient hemiplegia, and yawning.

Respiratory

influenza and diseases of the lower respiratory tract and lower respiratory tract infection.

Skin

Skin eruption, herpes, and peeling of the skin.

Urogenital

Disorder of breasts, endometriosis, and renal calculus.

Postmarketing Experience (Reports for Subcutaneous or Oral Sumatriptan)

The following section enumerates potentially important adverse events that have occurred in clinical practice and that have been reported spontaneously to various surveillance systems. The events enumerated represent reports arising from both domestic and nondomestic use of oral or subcutaneous dosage forms of sumatriptan. The events enumerated include all except those already listed in the ADVERSE REACTIONS section above or those too general to be informative. Because the reports cite events reported spontaneously from worldwide postmarketing experience, frequency of events and the role of sumatriptan in their causation cannot be reliably determined. It is assumed, however, that systemic reactions following sumatriptan use are likely to be similar regardless of route of administration.

Blood

Hemolytic anemia, pancytopenia, thrombocytopenia.

Cardiovascular

Atrial fibrillation, cardiomyopathy, colonic ischemia (see WARNINGS), Prinzmetal variant angina, pulmonary embolism, shock, thrombophlebitis.

Ear, Nose, and Throat

Deafness.

Eye

Ischemic optic neuropathy, retinal artery occlusion, retinal vein thrombosis, loss of vision.

Gastrointestinal

Ischemic colitis with rectal bleeding (see WARNINGS), xerostomia.

Hepatic

Elevated liver function tests.

Neurological

Central nervous system vasculitis, cerebrovascular accident, dysphasia, serotonin syndrome, subarachnoid hemorrhage.

Non-Site Specific

Angioneurotic edema, cyanosis, death (see WARNINGS), temporal arteritis.

Psychiatry

Panic disorder.

Respiratory

Bronchospasm in patients with and without a history of asthma.

Skin

Exacerbation of sunburn, hypersensitivity reactions (allergic vasculitis, erythema, pruritus, rash, shortness of breath, urticaria; in addition, severe anaphylaxis/anaphylactoid reactions have been reported [see WARNINGS]), photosensitivity.

Urogenital

Acute renal failure.

DRUG ABUSE AND DEPENDENCE

One clinical study with sumatriptan succinate injection enrolling 12 patients with a history of substance abuse failed to induce subjective behavior and/or physiologic response ordinarily associated with drugs that have an established potential for abuse.

OVERDOSAGE

Patients (N = 670) have received single oral doses of 140 to 300 mg without significant adverse effects. Volunteers (N = 174) have received single oral doses of 140 to 400 mg without serious adverse events.

Overdose in animals has been fatal and has been heralded by convulsions, tremor, paralysis, inactivity, ptosis, erythema of the extremities, abnormal respiration, cyanosis, ataxia, mydriasis, salivation, and lacrimation. The elimination half-life of sumatriptan is approximately 2.5 hours (see CLINICALPHARMACOLOGY), and therefore monitoring of patients after overdose with sumatriptan tablets should continue for at least 12 hours or while symptoms or signs persist.

It is unknown what effect hemodialysis or peritoneal dialysis has on the serum concentrations of sumatriptan.

DOSAGE AND ADMINISTRATION

In controlled clinical trials, single doses of 25, 50, or 100 mg of sumatriptan tablets were effective for the acute treatment of migraine in adults. There is evidence that doses of 50 and 100 mg may provide a greater effect than 25 mg (see CLINICALTRIALS). There is also evidence that doses of 100 mg do not provide a greater effect than 50 mg. Individuals may vary in response to doses of sumatriptan tablets. The choice of dose should therefore be made on an individual basis, weighing the possible benefit of a higher dose with the potential for a greater risk of adverse events.

If the headache returns or the patient has a partial response to the initial dose, the dose may be repeated after 2 hours, not to exceed a total daily dose of 200 mg. If a headache returns following an initial treatment with sumatriptan succinate injection, additional single sumatriptan tablets (up to 100 mg/day) may be given with an interval of at least 2 hours between tablet doses. The safety of treating an average of more than 4 headaches in a 30-day period has not been established.

Because of the potential of MAO-A inhibitors to cause unpredictable elevations in the bioavailability of oral sumatriptan, their combined use is contraindicated (see CONTRAINDICATIONS).

Hepatic disease/functional impairment may also cause unpredictable elevations in the bioavailability of orally administered sumatriptan. Consequently, if treatment is deemed advisable in the presence of liver disease, the maximum single dose should in general not exceed 50 mg (see CLINICALPHARMACOLOGYfor the basis of this recommendation).

HOW SUPPLIED

Sumatriptan tablets USP, 25, 50, and 100 mg of sumatriptan (base) as the succinate.

Sumatriptan tablets USP, 25 mg are white, round, biconvex film-coated tablets debossed with “RDY” on one side and “291” on the other side. The tablets are supplied in bottles of 30, 36, 90 100, 500, unit of use blister pack of 9's and unit dose package of 100's.

Bottles of 30 NDC 55111-291-30

Bottles of 36 NDC 55111-291-36

Bottles of 90 NDC 55111-291-90

Bottles of 100 NDC 55111-291-01

Bottles of 500 NDC 55111-291-05

Unit of use blister pack of 9 (1 x 9) NDC 55111-291-09

Unit dose package of 100 (10 x 10) NDC 55111-291-78

Sumatriptan tablets USP, 50 mg are white, round, biconvex film-coated tablets debossed with “RDY” on one side and “292” on the other side. The tablets are supplied in bottles of 30, 36, 90 100, 500, unit of use blister pack of 9's and unit dose package of 100's.

Bottles of 30 NDC 55111-292-30

Bottles of 36 NDC 55111-292-36

Bottles of 90 NDC 55111-292-90

Bottles of 100 NDC 55111-292-01

Bottles of 500 NDC 55111-292-05

Unit of use blister pack of 9 (1 x 9) NDC 55111-292-09

Unit dose package of 100 (10 x 10) NDC 55111-292-78

Sumatriptan tablets USP, 100 mg are white, capsule shaped, biconvex film-coated tablets debossed with “RDY” on one side and “293” on the other side. The tablets are supplied in bottles of 30, 36, 90 100, 500, unit of use blister pack of 9's and unit dose package of 100's.

Bottles of 30 NDC 55111-293-30

Bottles of 36 NDC 55111-293-36

Bottles of 90 NDC 55111-293-90

Bottles of 100 NDC 55111-293-01

Bottles of 500 NDC 55111-293-05

Unit of use blister pack of 9 (1 x 9) NDC 55111-293-09

Unit dose package of 100 (10 x 10) NDC 55111-293-78

Store at 20 to 25°C (68 – 77°F) [See USP Controlled Room Temperature].

Dispense in a tight, light-resistant container as defined in the USP, with a child-resistant closure (as required).

ANIMAL TOXICOLOGY

Corneal Opacities

Dogs receiving oral sumatriptan developed corneal opacities and defects in the corneal epithelium. Corneal opacities were seen at the lowest dosage tested, 2 mg/kg/day, and were present after 1 month of treatment. Defects in the corneal epithelium were noted in a 60-week study. Earlier examinations for these toxicities were not conducted and no-effect doses were not established; however, the relative exposure at the lowest dose tested was approximately 5 times the human exposure after a 100 mg oral dose. There is evidence of alterations in corneal appearance on the first day of intranasal dosing to dogs. Changes were noted at the lowest dose tested, which was approximately one half the maximum single human oral dose of 100 mg on a mg/m^2 basis.

RX Only

Manufactured by:

Dr. Reddy’s Laboratories Limited

Bachepalli – 502 325 INDIA

Revised: 0312

PATIENT PACKAGE INSERT

Patient Information

Sumatriptan Tablets USP

Read this Patient Information before you start taking sumatriptan tablets and each time you get a refill. There may be new information. This information does not take the place of talking with your healthcare provider about your medical condition or treatment.

What is the most important information I should know about sumatriptan tablets?

Sumatriptan tablets can cause serious side effects, including: Heart attack and other heart problems. Heart problems may lead to death.

Stop taking sumatriptan tablets and get emergency medical help right away if you have any of the following symptoms of a heart attack:

- discomfort in the center of your chest that lasts for more than a few minutes, or that goes away and comes back
- chest pain or chest discomfort that feels like uncomfortable heavy pressure, squeezing, or fullness, or pain
- pain or discomfort in your arms, back, neck, jaw, or stomach
- shortness of breath with or without chest discomfort
- breaking out in a cold sweat
- nausea or vomiting
- feeling lightheaded

Sumatriptan tablets are not for people with risk factors for heart disease unless a heart exam is done and shows no problem. You have a higher risk for heart disease if you:

- have high blood pressure
- have high cholesterol levels
- smoke
- are overweight
- have diabetes
- have a family history of heart disease
- are a female who has gone through menopause
- are a male over age 40

Serotonin syndrome. Serotonin syndrome is a serious and life-threatening problem that can happen in people taking sumatriptan tablets, especially if sumatriptan tablets are used with antidepressant medicines called selective serotonin reuptake inhibitors (SSRIs) or selective norepinephrine reuptake inhibitors (SNRIs).

Ask your healthcare provider or pharmacist for a list of these medicines if you are not sure.

Call your healthcare provider right away if you have any of the following symptoms of serotonin syndrome:

- mental changes such as seeing things that are not there (hallucinations), agitation, or coma
- fast heartbeat
- changes in blood pressure
- high body temperature
- tight muscles
- trouble walking
- nausea, vomiting, or diarrhea

What are sumatriptan tablets?

Sumatriptan tablets are a prescription medicine used to treat acute migraine headaches with or without aura in adults.

Sumatriptan tablets are not used to prevent or decrease the number of migraine headaches you have.

Sumatriptan tablets are not used to treat other types of headaches such as hemiplegic (that make you unable to move on one side of your body) or basilar migraines (rare form of migraine with aura).

It is not known if sumatriptan tablets are safe and effective to treat cluster headaches.

It is not known if sumatriptan tablets are safe and effective in children under 18 years of age.

Who should not take sumatriptan tablets?

Do not take sumatriptan tablets if you have:

- heart problems or a history of heart problems
- narrowing of blood vessels to your legs, arms, stomach, or kidney (peripheral vascular disease)
- uncontrolled high blood pressure
- severe liver problems
- hemiplegic migraines or basilar migraines. If you are not sure if you have these types of migraines, ask your healthcare provider.
- had a stroke, transient ischemic attacks (TIAs), or problems with your blood circulation
- taken any of the following medicines in the last 24 hours:
- almotriptan (AXERT®)
- eletriptan (RELPAX®)
- frovatriptan (FROVA®)
- naratriptan (AMERGE®)
- rizatriptan (MAXALT®, MAXALT-MLT®)
- sumatriptan and naproxen (TREXIMET®)
- ergotamines (CAFERGOT®, ERGOMAR®, MIGERGOT®)
- dihydroergotamine (D.H.E. 45®, MIGRANAL®)

Ask your doctor if you are not sure if your medicine is listed above.

- an allergy to sumatriptan or any of the ingredients in sumatriptan tablets. See the end of this leaflet for a complete list of ingredients in sumatriptan tablets.

What should I tell my healthcare provider before taking sumatriptan tablets?

Before you take sumatriptan tablets, tell your healthcare provider about all of your medical conditions, including if you:

- have high blood pressure
- have high cholesterol
- have diabetes
- smoke
- are overweight
- are a female who has gone through menopause
- have heart disease or a family history of heart disease or stroke
- have kidney problems
- have liver problems
- have had epilepsy or seizures
- are not using effective birth control
- are pregnant or plan to become pregnant. It is not known if sumatriptan tablets will harm your unborn baby.
- are breastfeeding or plan to breastfeed. Sumatriptan tablets passes into your breast milk and may harm your baby. Talk with your healthcare provider about the best way to feed your baby if you take sumatriptan tablets.

Tell your healthcare provider about all the medicines you take, including prescription and nonprescription medicines, vitamins, and herbal supplements.

Sumatriptan tablets and other medicines may affect each other, causing side effects.

Especially tell your healthcare provider if you take anti-depressant medicines called:

- selective serotonin reuptake inhibitors (SSRIs)
- serotonin norepinephrine reuptake inhibitors (SNRIs)
- monoamine oxidase inhibitors (MAOIs)

Ask your healthcare provider or pharmacist for a list of these medicines if you are not sure.

Know the medicines you take. Keep a list of them to show your healthcare provider or pharmacist when you get a new medicine.

How should I take sumatriptan tablets?

- Certain people should take their first dose of sumatriptan tablets in their healthcare provider’s office or in another medical setting. Ask your healthcare provider if you should take your first dose in a medical setting.
- Take sumatriptan tablets exactly as your healthcare provider tells you to take it.
- Your healthcare provider may change your dose. Do not change your dose without first talking to your healthcare provider.
- Take sumatriptan tablets with water or other liquids.
- If you do not get any relief after your first sumatriptan tablet, do not take a second tablet without first talking with your healthcare provider.
- If your headache comes back or you only get some relief from your headache, you can take a second tablet 2 hours after the first tablet
- Do not take more than a total of 200 mg of sumatriptan tablets in a 24-hour period.
- Some people who take too many sumatriptan tablets may have worse headaches (medication overuse headache). If your headaches get worse, your healthcare provider may decide to stop your treatment with sumatriptan tablets.
- If you take too much sumatriptan tablets, call your healthcare provider or go to the nearest hospital emergency room right away.
- You should write down when you have headaches and when you take sumatriptan tablets so you can talk with your healthcare provider about how sumatriptan tablets are working for you.

What should I avoid while taking sumatriptan tablets?

Sumatriptan tablets can cause dizziness, weakness, or drowsiness. If you have these symptoms, do not drive a car, use machinery, or do anything where you need to be alert.

What are the possible side effects of sumatriptan tablets? Sumatriptan tablets may cause serious side effects. See “What is the most important information I should know about sumatriptan tablets?”

These serious side effects include:

- changes in color or sensation in your fingers and toes (Raynaud’s syndrome)
- stomach and intestinal problems (gastrointestinal and colonic ischemic events). Symptoms of gastrointestinal and colonic ischemic events include:
- sudden or severe stomach pain
- stomach pain after meals
- weight loss
- nausea or vomiting
- constipation or diarrhea
- bloody diarrhea
- fever
- problems with blood circulation to your legs and feet (peripheral vascular ischemia). Symptoms of peripheral vascular ischemia include:
- cramping and pain in your legs or hips
- feeling of heaviness or tightness in your leg muscles
- burning or aching pain in your feet or toes while resting
- numbness, tingling, or weakness in your legs
- cold feeling or color changes in 1 or both legs or feet
- shortness of breath or wheezing
- hives (itchy bumps); swelling of your tongue, mouth, or throat

The most common side effects of sumatriptan tablets include:

- tingling or numbness in your fingers or toes
- dizziness
- warm, hot, burning feeling to your face (flushing)
- feeling weak, drowsy, or tired

Tell your healthcare provider if you have any side effect that bothers you or that does not go away.

These are not all the possible side effects of sumatriptan tablets. For more information, ask your healthcare provider or pharmacist.

Call your doctor for medical advice about side effects. You may report side effects to FDA at 1-800-FDA-1088.

How should I store Sumatriptan Tablets?

Store at 20 to 25°C (68 – 77°F) [See USP Controlled Room Temperature].

Dispense in a tight, light-resistant container as defined in the USP, with a child-resistant closure (as required).

Keep sumatriptan tablets and all medicines out of the reach of children.

General information about the safe and effective use of sumatriptan tablets.

Medicines are sometimes prescribed for purposes other than those listed in Patient Information leaflets. Do not use sumatriptan tablets for a condition for which it was not prescribed. Do not give sumatriptan tablets to other people, even if they have the same symptoms you have. It may harm them.

This Patient Information leaflet summarizes the most important information about sumatriptan tablets. If you would like more information, talk with your healthcare provider. You can ask your healthcare provider or pharmacist for information about sumatriptan tablets that is written for healthcare professionals.

For more information, call 1-888-375-3784.

What are the ingredients in Sumatriptan Tablets?

Active ingredients : Sumatriptan succinate

Inactive ingredients: croscarmellose sodium, lactose anhydrous, lactose monohydrate, magnesium stearate, mannitol, microcrystalline cellulose, talc, titanium dioxide and triacetin.

To reorder additional Patient Information Leaflets, please contact Dr. Reddy’s Customer Service at 1-866-733-3952.

IMITREX, AMERGE, and TREXIMET are registered trademarks of GlaxoSmithKline. The other brands listed are trademarks of their respective owners.

This Patient Information has been approved by the U.S. Food and Drug Administration.

RX Only

Manufactured by:

Dr. Reddy’s Laboratories Limited

Bachepalli – 502 325 INDIA

Revised : 0312

1 INDICATIONS AND USAGE

Ondansetron tablets are indicated for the prevention of nausea and vomiting associated with:
• highly emetogenic cancer chemotherapy, including cisplatin greater than or equal to 50 mg/m^2.
• initial and repeat courses of moderately emetogenic cancer chemotherapy.
• radiotherapy in patients receiving either total body irradiation, single high-dose fraction to the abdomen, or daily fractions to the abdomen.

Ondansetron tablets are also indicated for the prevention of postoperative nausea and/or vomiting.

2 DOSAGE AND ADMINISTRATION

2.1 Dosage

The recommended dosage regimens for adult and pediatric patients are described in Table 1 and Table 2, respectively.
Table 1: Adult Recommended Dosage Regimen for Prevention of Nausea and Vomiting

Indication | Dosage Regimen
Highly Emetogenic Cancer Chemotherapy | A single 24 mg dose administered 30 minutes before the start of single-day highly emetogenic chemotherapy, including cisplatin greater than or equal to 50 mg/m^2
Moderately Emetogenic Cancer Chemotherapy | 8 mg administered 30 minutes before the start of chemotherapy, with a subsequent 8 mg dose 8 hours after the first dose. Then administer 8 mg twice a day (every 12 hours) for 1 to 2 days after completion of chemotherapy
Radiotherapy | For total body irradiation: 8 mg administered 1 to 2 hours before each fraction of radiotherapy each day. For single high-dose fraction radiotherapy to the abdomen: 8 mg administered 1 to 2 hours before radiotherapy, with subsequent 8 mg doses every 8 hours after the first dose for 1 to 2 days after completion of radiotherapy. For daily fractionated radiotherapy to the abdomen: 8 mg administered 1 to 2 hours before radiotherapy, with subsequent 8 mg doses every 8 hours after the first dose for each day radiotherapy is given.
Postoperative | 16 mg administered 1 hour before induction of anesthesia

Table 2: Pediatric Recommended Dosage Regimen for Prevention of Nausea and Vomiting

Indication | Dosage Regimen
Moderately Emetogenic Cancer Chemotherapy | 12 to 17 years of age: 8 mg administered 30 minutes before the start of chemotherapy, with a subsequent 8 mg dose 4 and 8 hours after the first dose. Then administer 8 mg three times a day for 1 to 2 days after completion of chemotherapy. 4 to 11 years of age: 4 mg administered 30 minutes before the start of chemotherapy, with a subsequent 4 mg dose 4 and 8 hours after the first dose. Then administer 4 mg three times a day for 1 to 2 days after completion of chemotherapy.

2.2 Dosage in Hepatic Impairment

In patients with severe hepatic impairment (Child-Pugh score of 10 or greater), do not exceed a total daily dose of 8 mg [see Use in Specific Populations (8.6), Clinical Pharmacology (12.3)].

3 DOSAGE FORMS AND STRENGTHS

Ondansetron Tablets USP, are available in the following strengths:
• 4 mg – white, oval, film-coated tablets engraved with "4" on one side and “NO” on other side.
• 8 mg – yellow, oval, film-coated tablets engraved with "8" on one side and "NO" on the other side.

4 CONTRAINDICATIONS

Ondansetron tablets are contraindicated in patients:
• known to have hypersensitivity (e.g., anaphylaxis) to ondansetron or any of the components of the formulation [see Adverse Reactions (6.2)].
• receiving concomitant apomorphine due to the risk of profound hypotension and loss of consciousness.

5 WARNINGS AND PRECAUTIONS

5.1 Hypersensitivity Reactions

Hypersensitivity reactions, including anaphylaxis and bronchospasm, have been reported in patients who have exhibited hypersensitivity to other selective 5-HT3 receptor antagonists. If hypersensitivity reactions occur, discontinue use of ondansetron tablets; treat promptly per standard of care and monitor until signs and symptoms resolve [see Contraindications (4)].

5.2 QT Prolongation

Electrocardiogram (ECG) changes including QT interval prolongation have been seen in patients receiving ondansetron. In addition, postmarketing cases of Torsade de Pointes have been reported in patients using ondansetron tablets. Avoid ondansetron tablets in patients with congenital long QT syndrome. ECG monitoring is recommended in patients with electrolyte abnormalities (e.g., hypokalemia or hypomagnesemia), congestive heart failure, bradyarrhythmias, or patients taking other medicinal products that lead to QT prolongation [see Clinical Pharmacology (12.2)].

5.3 Serotonin Syndrome

The development of serotonin syndrome has been reported with 5-HT3 receptor antagonists alone. Most reports have been associated with concomitant use of serotonergic drugs (e.g., selective serotonin reuptake inhibitors (SSRIs), serotonin and norepinephrine reuptake inhibitors (SNRIs), monoamine oxidase inhibitors, mirtazapine, fentanyl, lithium, tramadol, and intravenous methylene blue). Some of the reported cases were fatal. Serotonin syndrome occurring with overdose of ondansetron tablets alone has also been reported. The majority of reports of serotonin syndrome related to 5-HT3 receptor antagonist use occurred in a post-anesthesia care unit or an infusion center.
Symptoms associated with serotonin syndrome may include the following combination of signs and symptoms: mental status changes (e.g., agitation, hallucinations, delirium, and coma), autonomic instability (e.g., tachycardia, labile blood pressure, dizziness, diaphoresis, flushing, hyperthermia), neuromuscular symptoms (e.g., tremor, rigidity, myoclonus, hyperreflexia, incoordination), seizures, with or without gastrointestinal symptoms (e.g., nausea, vomiting, diarrhea). Patients should be monitored for the emergence of serotonin syndrome, especially with concomitant use of ondansetron tablets and other serotonergic drugs. If symptoms of serotonin syndrome occur, discontinue ondansetron tablets and initiate supportive treatment. Patients should be informed of the increased risk of serotonin syndrome, especially if ondansetron tablets is used concomitantly with other serotonergic drugs [see Drug Interactions (7.1), Overdosage (10)].

5.4 Masking of Progressive Ileus and Gastric Distension

The use of ondansetron tablets in patients following abdominal surgery or in patients with chemotherapy-induced nausea and vomiting may mask a progressive ileus and/or gastric distension. Monitor for decreased bowel activity, particularly in patients with risk factors for gastrointestinal obstruction.
Ondansetron tablets are not a drug that stimulates gastric or intestinal peristalsis. It should not be used instead of nasogastric suction.

6 ADVERSE REACTIONS

6.1 Clinical Trials Experience

Because clinical trials are conducted under widely varying conditions, adverse reaction rates observed in the clinical trials of a drug cannot be directly compared with rates in the clinical trials of another drug and may not reflect the rates observed in practice.
The following adverse reactions have been reported in clinical trials of patients treated with ondansetron, the active ingredient of ondansetron tablets. A causal relationship to therapy with ondansetron tablets was unclear in many cases.
Prevention of Chemotherapy-induced Nausea and Vomiting
The most common adverse reactions reported in greater than or equal to 4% of 300 adults receiving a single 24 mg dose of ondansetron tablets orally in 2 trials for the prevention of nausea and vomiting associated with highly emetogenic chemotherapy (cisplatin greater than or equal to 50 mg/m^2) were: headache (11%) and diarrhea (4%).
The most common adverse reactions reported in 4 trials in adults for the prevention of nausea and vomiting associated with moderately emetogenic chemotherapy (primarily cyclophosphamide-based regimens) are shown in Table 3.
Table 3. Most Common Adverse Reactions in Adultsa for the Prevention of Nausea and Vomiting Associated with Moderately Emetogenic Chemotherapy [Primarily Cyclophosphamide-based Regimens]

Adverse Reaction | Ondansetron Tablets 8 mg Twice Daily (n = 242) | Placebo (n = 262)
Headache | 58 (24%) | 34 (13%)
Malaise/fatigue | 32 (13%) | 6 (2%)
Constipation | 22 (9%) | 1 (<1%)
Diarrhea | 15 (6%) | 10 (4%)
a Reported in greater than or equal to 5% of patients treated with ondansetron tablets and at a rate that exceeded placebo.

Less Common Adverse Reactions
Central Nervous System: Extrapyramidal reactions (less than 1% of patients).
Hepatic: Aspartate transaminase (AST) and/or alanine transaminase (ALT) values exceeded twice the upper limit of normal in approximately 1% to 2% of 723 patients receiving ondansetron tablets and cyclophosphamide-based chemotherapy in US clinical trials. The increases were transient and did not appear to be related to dose or duration of therapy. On repeat exposure, similar transient elevations in transaminase values occurred in some courses, but symptomatic hepatic disease did not occur. The role of cancer chemotherapy in these biochemical changes is unclear.
Liver failure and death has been reported in cancer patients receiving concurrent medications, including potentially hepatotoxic cytotoxic chemotherapy and antibiotics. The etiology of the liver failure is unclear.
Integumentary: Rash (approximately 1% of patients).
Other (less than 2%): Anaphylaxis, bronchospasm, tachycardia, angina, hypokalemia, electrocardiographic alterations, vascular occlusive events, and grand mal seizures. Except for bronchospasm and anaphylaxis, the relationship to ondansetron tablets is unclear.
Prevention of Radiation-induced Nausea and Vomiting
The most common adverse reactions (greater than or equal to 2%) reported in patients receiving ondansetron tablets and concurrent radiotherapy were similar to those reported in patients receiving ondansetron tablets and concurrent chemotherapy and were headache, constipation, and diarrhea.
Prevention of Postoperative Nausea and Vomiting
The most common adverse reactions reported in adults in trial(s) of prevention of postoperative nausea and vomiting are shown in Table 4. In these trial(s) patients were receiving multiple concomitant perioperative and postoperative medications in both treatment groups.
Table 4. Most Common Adverse Reactions in Adultsa for the Prevention of Postoperative Nausea and Vomiting

Adverse Reaction | Ondansetron Tablets 16 mg as a Single Dose (n = 550) | Placebo (n = 531)
Headache | 49 (9%) | 27 (5%)
Hypoxia | 49 (9%) | 35 (7%)
Pyrexia | 45 (8%) | 34 (6%)
Dizziness | 36 (7%) | 34 (6%)
Gynecological disorder | 36 (7%) | 33 (6%)
Anxiety/agitation | 33 (6%) | 29 (5%)
Urinary retention | 28 (5%) | 18 (3%)
Pruritus | 27 (5%) | 20 (4%)
a Reported in greater than or equal to 5% of patients treated with ondansetron tablets and at a rate that exceeded placebo.

6.2 Postmarketing Experience

The following adverse reactions have been identified during post-approval use of ondansetron. Because these reactions are reported voluntarily from a population of uncertain size, it is not always possible to reliably estimate their frequency or establish a causal relationship to drug exposure.
Cardiovascular
Arrhythmias (including ventricular and supraventricular tachycardia, premature ventricular contractions, and atrial fibrillation), bradycardia, electrocardiographic alterations (including second-degree heart block, QT/QTc interval prolongation, and ST segment depression), palpitations, and syncope. Rarely and predominantly with intravenous ondansetron, transient ECG changes including QT interval prolongation have been reported.
General
Flushing. Rare cases of hypersensitivity reactions, sometimes severe (e.g., anaphylactic reactions, angioedema, bronchospasm, shortness of breath, hypotension, laryngeal edema, stridor) have also been reported.
Laryngospasm, shock, and cardiopulmonary arrest have occurred during allergic reactions in patients receiving injectable ondansetron.
Hepatobiliary
Liver enzyme abnormalities.
Lower Respiratory
Hiccups.
Neurology
Oculogyric crisis, appearing alone, as well as with other dystonic reactions.
Skin
Urticaria, Stevens-Johnson syndrome, and toxic epidermal necrolysis.
Eye Disorders
Cases of transient blindness, predominantly during intravenous administration, have been reported. These cases of transient blindness were reported to resolve within a few minutes up to 48 hours.

7 DRUG INTERACTIONS

7.1 Serotonergic Drugs

Serotonin syndrome (including altered mental status, autonomic instability, and neuromuscular symptoms) has been described following the concomitant use of 5-HT3 receptor antagonists and other serotonergic drugs, including selective serotonin reuptake inhibitors (SSRIs) and serotonin and noradrenaline reuptake inhibitors (SNRIs). Monitor for the emergence of serotonin syndrome. If symptoms occur, discontinue ondansetron tablets and initiate supportive treatment [see Warnings and Precautions (5.3)].

7.2 Drugs Affecting Cytochrome P-450 Enzymes

Ondansetron does not itself appear to induce or inhibit the cytochrome P-450 drug-metabolizing enzyme system of the liver [see Clinical Pharmacology (12.3)]. Because ondansetron is metabolized by hepatic cytochrome P-450 drug-metabolizing enzymes (CYP3A4, CYP2D6, CYP1A2), inducers or inhibitors of these enzymes may change the clearance and, hence, the half-life of ondansetron. In patients treated with potent inducers of CYP3A4 (i.e., phenytoin, carbamazepine, and rifampin), the clearance of ondansetron was significantly increased and ondansetron blood concentrations were decreased. However, on the basis of available data, no dosage adjustment for ondansetron tablets is recommended for patients on these drugs [see Clinical Pharmacology (12.3)].

7.3 Tramadol

Although no pharmacokinetic drug interaction between ondansetron and tramadol has been observed, data from 2 small trials indicate that when used together, ondansetron tablets may increase patient-controlled administration of tramadol. Monitor patients to ensure adequate pain control when ondansetron is administered with tramadol.

7.4 Chemotherapy

Carmustine, etoposide, and cisplatin do not affect the pharmacokinetics of ondansetron.
In a crossover trial in 76 pediatric patients, intravenous ondansetron did not increase systemic concentrations of high-dose methotrexate.

7.5 Alfentanil and Atracurium

Ondansetron tablets do not alter the respiratory depressant effects produced by alfentanil or the degree of neuromuscular blockade produced by atracurium. Interactions with general or local anesthetics have not been studied.

8 USE IN SPECIFIC POPULATIONS

8.1 Pregnancy

Risk Summary
Available data do not reliably inform the association of ondansetron tablets and adverse fetal outcomes. Published epidemiological studies on the association between ondansetron and fetal outcomes have reported inconsistent findings and have important methodological limitations hindering interpretation [see Data]. Reproductive studies in rats and rabbits did not show evidence of harm to the fetus when ondansetron was administered during organogenesis at approximately 6 and 24 times the maximum recommended human oral dose of 24 mg/day, based on body surface area, respectively [see Data].
The background risk of major birth defects and miscarriage for the indicated population is unknown. In the US general population, the estimated background risk of major birth defects and miscarriages in clinically recognized pregnancies is 2 to 4% and 15 to 20%, respectively.
Data
Human Data
Methodological limitations of the epidemiology studies preclude a reliable evaluation of the potential risk of adverse fetal outcomes with the use of ondansetron in pregnancy.
Two large retrospective cohort studies of ondansetron use in pregnancy have been published. In one study with 1,349 infants born to women who reported the use of ondansetron or received an ondansetron prescription in the first trimester, no increased risk for major congenital malformations was seen in aggregate analysis. In this same study, however, a sub-analysis for specific malformations reported an association between ondansetron exposure and cardiovascular defect (odds ratio (OR) 1.62 [95% CI (1.04, 2.14)]) and cardiac septal defect (OR) 2.05 [95% CI (1.19, 3.28)]). The second study examined 1970 women who received ondansetron prescription during pregnancy and reported no association between ondansetron exposure and major congenital malformations, miscarriage or stillbirth, and infants of low birth weight or small for gestational age. Important methodological limitations with these studies include the uncertainty of whether women who filled a prescription actually took the medication, the concomitant use of other medications or treatments, and other unadjusted confounders that may account for the study findings.
A case-control study evaluating associations between several common non-cardiac malformations and multiple antiemetic drugs reported an association between maternal use of ondansetron and isolated cleft palate (reported adjusted OR = 2.37 [95% CI (1.18, 4.76)]). However, this association could be a chance finding, given the large number of drugs-birth defect comparisons in this study. It is unknown whether ondansetron exposure in utero in the cases of cleft palate occurred during the time of palate formation (the palate is formed between the 6th and 9th weeks of pregnancy) or whether mothers of infants with cleft palate used other medications or had other risk factors for cleft palate in the offspring. In addition, no cases of isolated cleft palate were identified in the aforementioned two large retrospective cohort studies. At this time, there is no clear evidence that ondansetron exposure in early pregnancy can cause cleft palate.
Animal Data
In embryo-fetal development studies in rats and rabbits, pregnant animals received oral doses of ondansetron up to 15 mg/kg/day and 30 mg/kg/day, respectively, during the period of organogenesis. With the exception of a slight decrease in maternal body weight gain in the rabbits, there were no significant effects of ondansetron on the maternal animals or the development of the offspring. At doses of 15 mg/kg/day in rats and 30 mg/kg/day in rabbits, the maternal exposure margin was approximately 6 and 24 times the maximum recommended human oral dose of 24 mg/day, respectively, based on body surface area.
In a pre-and postnatal developmental toxicity study, pregnant rats received oral doses of ondansetron up to 15 mg/kg/day from Day 17 of pregnancy to litter Day 21. With the exception of a slight reduction in maternal body weight gain, there were no effects upon the pregnant rats and the pre-and postnatal development of their offspring, including reproductive performance of the mated F1 generation. At a dose of 15 mg/kg/day in rats, the maternal exposure margin was approximately 6 times the maximum recommended human oral dose of 24 mg/day, based on body surface area.

8.2 Lactation

Risk Summary
It is not known whether ondansetron is present in human milk. There are no data on the effects of ondansetron tablets on the breastfed infant or the effects on milk production. However, it has been demonstrated that ondansetron is present in the milk of rats.

The developmental and health benefits of breastfeeding should be considered along with the mother’s clinical need for ondansetron tablets and any potential adverse effects on the breast-fed infant from ondansetron tablets or from the underlying maternal condition.

8.4 Pediatric Use

The safety and effectiveness of orally administered ondansetron tablets have been established in pediatric patients 4 years and older for the prevention of nausea and vomiting associated with moderately emetogenic cancer chemotherapy. Use of ondansetron tablets in these age-groups is supported by evidence from adequate and well-controlled studies of ondansetron tablets in adults with additional data from 3 open-label, uncontrolled, non-US trials in 182 pediatric patients aged 4 to 18 years with cancer who were given a variety of cisplatin or noncisplatin regimens [see Dosage and Administration (2.2), Clinical Studies (14.1)].

Additional information on the use of ondansetron in pediatric patients may be found in ondansetron injection prescribing information.
The safety and effectiveness of orally administered ondansetron tablets have not been established in pediatric patients for:

- prevention of nausea and vomiting associated with highly emetogenic cancer chemotherapy.
- prevention of nausea and vomiting associated with radiotherapy.
- prevention of postoperative nausea and/or vomiting.

8.5 Geriatric Use

Of the total number of subjects enrolled in cancer chemotherapy-induced and postoperative nausea and vomiting in US-and foreign-controlled clinical trials, for which there were subgroup analyses, 938 (19%) were aged 65 years and older.

No overall differences in safety or effectiveness were observed between subjects 65 years of age and older and younger subjects. A reduction in clearance and increase in elimination half-life were seen in patients older than 75 years compared with younger subjects [see Clinical Pharmacology (12.3)].There were an insufficient number of patients older than 75 years of age and older in the clinical trials to permit safety or efficacy conclusions in this age-group. Other reported clinical experience has not identified differences in responses between the elderly and younger patients, but greater sensitivity of some older individuals cannot be ruled out. No dosage adjustment is needed in elderly patients.

8.6 Hepatic Impairment

No dosage adjustment is needed in patients with mild or moderate hepatic impairment.
In patients with severe hepatic impairment, clearance is reduced and the apparent volume of distribution is increased, resulting in a significant increase in the half-life of ondansetron. Therefore, do not exceed a total daily dose of 8 mg in patients with severe hepatic impairment (Child-Pugh score of 10 or greater) [see Dosage and Administration (2.2), Clinical Pharmacology (12.3)].

8.7 Renal Impairment

No dosage adjustment is recommended for patients with any degree of renal impairment (mild, moderate, or severe). There is no experience beyond first-day administration of ondansetron [see Clinical Pharmacology (12.3)].

9 DRUG ABUSE AND DEPENDENCE

Animal studies have shown that ondansetron is not discriminated as a benzodiazepine nor does it substitute for benzodiazepines in direct addiction studies.

10 OVERDOSAGE

There is no specific antidote for ondansetron overdose. Patients should be managed with appropriate supportive therapy.

In addition to the adverse reactions listed above, the following adverse reactions have been described in the setting of ondansetron overdose: “Sudden blindness” (amaurosis) of 2 to 3 minutes’ duration plus severe constipation occurred in one patient that was administered 72 mg of ondansetron intravenously as a single dose. Hypotension (and faintness) occurred in a patient that took 48 mg of ondansetron tablets. Following infusion of 32 mg over only a 4-minute period, a vasovagal episode with transient second-degree heart block was observed. In all instances, the adverse reactions resolved completely.

Pediatric cases consistent with serotonin syndrome have been reported after inadvertent oral overdoses of ondansetron (exceeding estimated ingestion of 5 mg per kg) in young children. Reported symptoms included somnolence, agitation, tachycardia, tachypnea, hypertension, flushing, mydriasis, diaphoresis, myoclonic movements, horizontal nystagmus, hyperreflexia, and seizure. Patients required supportive care, including intubation in some cases, with complete recovery without sequelae within 1 to 2 days.

11 DESCRIPTION

The active ingredient in ondansetron tablets is ondansetron hydrochloride as the dihydrate, the racemic form of ondansetron and a selective blocking agent of the serotonin 5-HT3 receptor type. Chemically it is (±) 1, 2, 3, 9-tetrahydro-9-methyl-3-[(2-methyl-1H-imidazol-1-yl) methyl]-4H-carbazol-4-one, monohydrochloride, dihydrate. It has the following structural formula:

The molecular formula is C18H19N3O•HCl•2H2O, representing a molecular weight of 365.5.

Ondansetron hydrochloride dihydrate is a white to off-white powder that is soluble in water and normal saline.

Each 4 mg ondansetron tablet, USP for oral administration contains ondansetron hydrochloride dihydrate equivalent to 4 mg of ondansetron. Each 8 mg ondansetron tablet, USP for oral administration contains ondansetron hydrochloride dihydrate equivalent to 8 mg of ondansetron. Each tablet also contains the inactive ingredients croscarmellose sodium, hypromellose, lactose monohydrate, magnesium stearate, microcrystalline cellulose, pregelatinized starch, titanium dioxide, triacetin, and iron oxide yellow (8 mg tablet only).

This product meets USP Dissolution Test 3.

12 CLINICAL PHARMACOLOGY

12.1 Mechanism of Action

Ondansetron is a selective 5-HT3 receptor antagonist. While its mechanism of action has not been fully characterized, ondansetron is not a dopamine-receptor antagonist. Serotonin receptors of the 5-HT3 type are present both peripherally on vagal nerve terminals and centrally in the chemoreceptor trigger zone of the area postrema. It is not certain whether ondansetron’s antiemetic action is mediated centrally, peripherally, or in both sites. However, cytotoxic chemotherapy appears to be associated with release of serotonin from the enterochromaffin cells of the small intestine. In humans, urinary 5-hydroxyindoleacetic acid (5-HIAA) excretion increases after cisplatin administration in parallel with the onset of emesis. The released serotonin may stimulate the vagal afferents through the 5-HT3 receptors and initiate the vomiting reflex.

12.2 Pharmacodynamics

In healthy subjects, single intravenous doses of 0.15 mg/kg of ondansetron had no effect on esophageal motility, gastric motility, lower esophageal sphincter pressure, or small intestinal transit time. Multiday administration of ondansetron has been shown to slow colonic transit in healthy subjects. Ondansetron has no effect on plasma prolactin concentrations.

Cardiac Electrophysiology
QTc interval prolongation was studied in a double-blind, single intravenous dose, placebo-and positive-controlled, crossover trial in 58 healthy subjects. The maximum mean (95% upper confidence bound) difference in QTcF from placebo after baseline correction was 19.5 (21.8) milliseconds and 5.6 (7.4) milliseconds after 15minute intravenous infusions of 32 mg and 8 mg of ondansetron injection, respectively. A significant exposure-response relationship was identified between ondansetron concentration and ΔΔQTcF. Using the established exposure-response relationship, 24 mg infused intravenously over 15 minutes had a mean predicted (95% upper prediction interval) ΔΔQTcF of 14.0 (16.3) milliseconds. In contrast, 16 mg infused intravenously over 15 minutes using the same model had a mean predicted (95% upper prediction interval) ΔΔQTcF of 9.1 (11.2) milliseconds. In this study, the 8 mg dose infused over 15 minutes did not prolong the QT interval to any clinically relevant extent.

12.3 Pharmacokinetics

Absorption
Ondansetron is absorbed from the gastrointestinal tract and undergoes some first-pass metabolism. Mean bioavailability in healthy subjects, following administration of a single 8 mg tablet, is approximately 56%.
Ondansetron systemic exposure does not increase proportionately to dose. The AUC from a 16 mg tablet was 24% greater than predicted from an 8 mg tablet dose. This may reflect some reduction of first-pass metabolism at higher oral doses.
Food Effects: Bioavailability is also slightly enhanced by the presence of food.
Distribution
Plasma protein binding of ondansetron as measured in vitro was 70% to 76% over the concentration range of 10 to 500 ng/mL. Circulating drug also distributes into erythrocytes.
Elimination
Metabolism and Excretion: Ondansetron is extensively metabolized in humans, with approximately 5% of a radiolabeled dose recovered as the parent compound from the urine. The metabolites are observed in the urine. The primary metabolic pathway is hydroxylation on the indole ring followed by subsequent glucuronide or sulphate conjugation.
In vitro metabolism studies have shown that ondansetron is a substrate for human hepatic cytochrome P-450 enzymes, including CYP1A2, CYP2D6, and CYP3A4. In terms of overall ondansetron turnover, CYP3A4 played the predominant role. Because of the multiplicity of metabolic enzymes capable of metabolizing ondansetron, it is likely that inhibition or loss of one enzyme (e.g., CYP2D6 genetic deficiency) will be compensated by others and may result in little change in overall rates of ondansetron elimination.
Although some nonconjugated metabolites have pharmacologic activity, these are not found in plasma at concentrations likely to significantly contribute to the biological activity of ondansetron.
Specific Populations
Age: Geriatric Population: A reduction in clearance and increase in elimination half-life are seen in patients older than 75 years compared to younger subjects [see Use in Specific Populations (8.5)].
Sex: Gender differences were shown in the disposition of ondansetron given as a single dose. The extent and rate of absorption are greater in women than men. Slower clearance in women, a smaller apparent volume of distribution (adjusted for weight), and higher absolute bioavailability resulted in higher plasma ondansetron concentrations. These higher plasma concentrations may in part be explained by differences in body weight between men and women. It is not known whether these sex-related differences were clinically important. More detailed pharmacokinetic information is contained in Tables 5 and 6.
Table 5. Pharmacokinetics in Male and Female Healthy Subjects after a Single Dose of a Ondansetron 8 mg Tablet

Age- group (years) Sex (M/F) | Mean Weight (kg) | N | Peak Plasma Concentration (ng/mL) | Time of Peak Plasma Concentration(h) | Mean Elimination Half- life (h) | Systemic Plasma Clearance L/h/kg | Absolute Bioavailability
18-40 M F | 69.0 62.7 | 6 5 | 26.2 42.7 | 2.0 1.7 | 3.1 3.5 | 0.403 0.354 | 0.483 0.663
61-74 M F | 77.5 60.2 | 6 6 | 24.1 52.4 | 2.1 1.9 | 4.1 4.9 | 0.384 0.255 | 0.585 0.643
≥75 M F | 78.0 67.6 | 5 6 | 37.0 46.1 | 2.2 2.1 | 4.5 6.2 | 0.277 0.249 | 0.619 0.747

Table 6. Pharmacokinetics in Male and Female Healthy Subjects after a Single Dose of a Ondansetron 24 mg Tablet

Age- group (years) Sex (M/F) | Mean Weight (kg) | N | Peak Plasma Concentration (ng/mL) | Time of Peak Plasma Concentration(h) | Mean Elimination Half- life (h)
18-43 M F | 84.1 71.8 | 8 8 | 125.8 194.4 | 1.9 1.6 | 4.7 5.8

Renal Impairment: Renal impairment is not expected to significantly influence the total clearance of ondansetron as renal clearance represents only 5% of the overall clearance. However, the mean plasma clearance of ondansetron was reduced by about 50% in patients with severe renal impairment (creatinine clearance less than 30 mL/min). The reduction in clearance was variable and not consistent with an increase in half-life [see Use in Specific Populations (8.7)].

Hepatic Impairment: In patients with mild-to-moderate hepatic impairment, clearance is reduced 2-fold and mean half-life is increased to 11.6 hours compared with 5.7 hours in healthy subjects. In patients with severe hepatic impairment (Child-Pugh score of 10 or greater), clearance is reduced 2-fold to 3-fold and apparent volume of distribution is increased with a resultant increase in half-life to 20 hours [see Dosage and Administration (2.2), Use in Specific Populations (8.6)].

Drug Interaction Studies
CYP3A4 Inducers: Ondansetron elimination may be affected by cytochrome P-450 inducers. In a pharmacokinetic trial of 16 epileptic patients maintained chronically on CYP3A4 inducers, carbamazepine, or phenytoin, a reduction in AUC, Cmax, and t½ of ondansetron was observed. This resulted in a significant increase in the clearance of ondansetron. However, this increase is not thought to be clinically relevant [see Drug Interactions (7.2)].

Chemotherapeutic Agents: Carmustine, etoposide, and cisplatin do not affect the pharmacokinetics of ondansetron [see Drug Interactions (7.4)].

Antacids: Concomitant administration of antacids does not alter the absorption of ondansetron.

13 NONCLINICAL TOXICOLOGY

13.1 Carcinogenesis, Mutagenesis, Impairment of Fertility

Carcinogenic effects were not seen in 2-year studies in rats and mice with oral ondansetron doses up to 10 mg/kg per day and 30 mg/kg per day, respectively (approximately 4 and 6 times the maximum recommended human oral dose of 24 mg per day, based on body surface area).

Ondansetron was not mutagenic in standard tests for mutagenicity.
Oral administration of ondansetron up to 15 mg/kg per day (approximately 6 times the maximum recommended human oral dose of 24 mg per day, based on body surface area) did not affect fertility or general reproductive performance of male and female rats.

14 CLINICAL STUDIES

Highly Emetogenic Chemotherapy
In two randomized, double-blind, monotherapy trials, a single 24 mg oral dose of ondansetron tablets was superior to a relevant historical placebo control in the prevention of nausea and vomiting associated with highly emetogenic cancer chemotherapy, including cisplatin greater than or equal to 50 mg/m^2. Steroid administration was excluded from these clinical trials. More than 90% of patients receiving a cisplatin dose ≥50 mg/m^2 in the historical placebo comparator experienced vomiting in the absence of antiemetic therapy.
The first trial compared oral doses of ondansetron 24 mg as a single dose, 8 mg every 8 hours for 2 doses, and 32 mg as a single dose in 357 adult cancer patients receiving chemotherapy regimens containing cisplatin greater than or equal to 50 mg/m^2. The first or single dose was administered 30 minutes prior to chemotherapy. A total of 66% of patients in the ondansetron 24 mg once-a-day group, 55% in the ondansetron 8 mg twice-a-day group, and 55% in the ondansetron 32 mg once-a-day group completed the 24-hour trial period with 0 emetic episodes and no rescue antiemetic medications, the primary endpoint of efficacy. Each of the 3 treatment groups was shown to be statistically significantly superior to a historical placebo control.
In the same trial, 56% of patients receiving a single 24 mg oral dose of ondansetron experienced no nausea during the 24-hour trial period, compared with 36% of patients in the oral ondansetron 8 mg twice-a-day group (P = 0.001) and 50% in the oral ondansetron 32 mg once-a-day group. Dosage regimens of ondansetron tablets 8 mg twice daily and 32 mg once daily are not recommended for the prevention of nausea and vomiting associated with highly emetogenic chemotherapy [see Dosage and Administration (2.1)].
In a second trial, efficacy of a single 24 mg oral dose of ondansetron tablets for the prevention of nausea and vomiting associated with highly emetogenic cancer chemotherapy, including cisplatin greater than or equal to 50 mg/m^2, was confirmed.
Moderately Emetogenic Chemotherapy
A randomized, placebo-controlled, double-blind trial was conducted in the US in 67 patients receiving a cyclophosphamide-based chemotherapy regimen containing doxorubicin. The first 8 mg dose of ondansetron tablets was administered 30 minutes before the start of chemotherapy, with a subsequent dose 8 hours after the first dose, followed by 8 mg of ondansetron tablets twice a day for 2 days after the completion of chemotherapy.
Ondansetron tablets were significantly more effective than placebo in preventing vomiting. Treatment response was based on the total number of emetic episodes over the 3-day trial period. The results of this trial are summarized in Table 7:
Table 7. Emetic Episodes: Treatment Response in Patients Receiving Moderately Emetogenic Chemotherapy (Cyclophosphamide-based Regimen Containing Doxorubicin)

 | Ondansetron Tablets (n = 33) | Placebo (n = 34) | P Value
Treatment response 0 Emetic episodes 1 to 2 Emetic episodes More than 2 emetic episodes/withdrawn | 20 (61%) 6 (18%) 7 (21%) | 2 (6%) 8 (24%) 24 (71%) | <0.001 <0.001
Median number of emetic episodes | 0.0 | Undefineda
Median time to first emetic episode (hours) | Undefinedb | 6.5
a Median undefined since at least 50% of the patients were withdrawn or had more than 2 emetic episodes.
b Median undefined since at least 50% of patients did not have any emetic episodes.

In a double-blind US trial in 336 patients receiving a cyclophosphamide-based chemotherapy regimen containing either methotrexate or doxorubicin, ondansetron tablets 8 mg administered twice a day was as effective as ondansetron tablets 8 mg administered 3 times a day in preventing nausea and vomiting. Ondansetron Tablets 8 mg three times daily is not a recommended regimen for the treatment of moderately emetogenic chemotherapy [see Dosage and Administration (2.1)].

Treatment response was based on the total number of emetic episodes over the 3-day trial period. See Table 8 for the details of the dosage regimens studied and results of this trial.
Table 8. Emetic Episodes: Treatment Response after Ondansetron Tablets Administered Twice a Day and Three Times a Day

14.1 Prevention of Chemotherapy-Induced Nausea and Vomiting

Highly Emetogenic Chemotherapy
In two randomized, double-blind, monotherapy trials, a single 24 mg oral dose of ondansetron tablets was superior to a relevant historical placebo control in the prevention of nausea and vomiting associated with highly emetogenic cancer chemotherapy, including cisplatin greater than or equal to 50 mg/m^2. Steroid administration was excluded from these clinical trials. More than 90% of patients receiving a cisplatin dose ≥50 mg/m^2 in the historical placebo comparator experienced vomiting in the absence of antiemetic therapy.
The first trial compared oral doses of ondansetron 24 mg as a single dose, 8 mg every 8 hours for 2 doses, and 32 mg as a single dose in 357 adult cancer patients receiving chemotherapy regimens containing cisplatin greater than or equal to 50 mg/m^2. The first or single dose was administered 30 minutes prior to chemotherapy. A total of 66% of patients in the ondansetron 24 mg once-a-day group, 55% in the ondansetron 8 mg twice-a-day group, and 55% in the ondansetron 32 mg once-a-day group completed the 24-hour trial period with 0 emetic episodes and no rescue antiemetic medications, the primary endpoint of efficacy. Each of the 3 treatment groups was shown to be statistically significantly superior to a historical placebo control.
In the same trial, 56% of patients receiving a single 24 mg oral dose of ondansetron experienced no nausea during the 24-hour trial period, compared with 36% of patients in the oral ondansetron 8 mg twice-a-day group (P = 0.001) and 50% in the oral ondansetron 32 mg once-a-day group. Dosage regimens of ondansetron tablets 8 mg twice daily and 32 mg once daily are not recommended for the prevention of nausea and vomiting associated with highly emetogenic chemotherapy [see Dosage and Administration (2.1)].
In a second trial, efficacy of a single 24 mg oral dose of ondansetron tablets for the prevention of nausea and vomiting associated with highly emetogenic cancer chemotherapy, including cisplatin greater than or equal to 50 mg/m^2, was confirmed.
Moderately Emetogenic Chemotherapy
A randomized, placebo-controlled, double-blind trial was conducted in the US in 67 patients receiving a cyclophosphamide-based chemotherapy regimen containing doxorubicin. The first 8 mg dose of ondansetron tablets was administered 30 minutes before the start of chemotherapy, with a subsequent dose 8 hours after the first dose, followed by 8 mg of ondansetron tablets twice a day for 2 days after the completion of chemotherapy.
Ondansetron tablets were significantly more effective than placebo in preventing vomiting. Treatment response was based on the total number of emetic episodes over the 3-day trial period. The results of this trial are summarized in Table 7:
Table 7. Emetic Episodes: Treatment Response in Patients Receiving Moderately Emetogenic Chemotherapy (Cyclophosphamide-based Regimen Containing Doxorubicin)

 | Ondansetron Tablets (n = 33) | Placebo (n = 34) | P Value
Treatment response 0 Emetic episodes 1 to 2 Emetic episodes More than 2 emetic episodes/withdrawn | 20 (61%) 6 (18%) 7 (21%) | 2 (6%) 8 (24%) 24 (71%) | <0.001 <0.001
Median number of emetic episodes | 0.0 | Undefineda
Median time to first emetic episode (hours) | Undefinedb | 6.5
a Median undefined since at least 50% of the patients were withdrawn or had more than 2 emetic episodes.
b Median undefined since at least 50% of patients did not have any emetic episodes.

In a double-blind US trial in 336 patients receiving a cyclophosphamide-based chemotherapy regimen containing either methotrexate or doxorubicin, ondansetron tablets 8 mg administered twice a day was as effective as ondansetron tablets 8 mg administered 3 times a day in preventing nausea and vomiting. Ondansetron Tablets 8 mg three times daily is not a recommended regimen for the treatment of moderately emetogenic chemotherapy [see Dosage and Administration (2.1)].

Treatment response was based on the total number of emetic episodes over the 3-day trial period. See Table 8 for the details of the dosage regimens studied and results of this trial.
Table 8. Emetic Episodes: Treatment Response after Ondansetron Tablets Administered Twice a Day and Three Times a Day

14.2 Radiation-Induced Nausea and Vomiting

Total Body Irradiation
In a randomized, placebo-controlled, double-blind trial in 20 patients, 8 mg of ondansetron tablets administered 1.5 hours before each fraction of radiotherapy for 4 days was significantly more effective than placebo in preventing vomiting induced by total body irradiation. Total body irradiation consisted of 11 fractions (120 cGy per fraction) over 4 days for a total of 1,320 cGy. Patients received 3 fractions for 3 days, then 2 fractions on Day 4.

Single High-dose Fraction Radiotherapy
In an active-controlled, double-blind trial in 105 patients receiving single high-dose radiotherapy (800 to 1,000 cGy) over an anterior or posterior field size of greater than or equal to 80 cm2 to the abdomen, ondansetron tablets was significantly more effective than metoclopramide with respect to complete control of emesis (0 emetic episodes). Patients received the first dose of ondansetron tablets (8 mg) or metoclopramide (10 mg) 1 to 2 hours before radiotherapy. If radiotherapy was given in the morning, 8 mg of ondansetron tablets or 10 mg of metoclopramide was administered in the late afternoon and repeated again before bedtime. If radiotherapy was given in the afternoon, patients took 8 mg of ondansetron tablets or 10 mg of metoclopramide only once before bedtime. Patients continued the doses of oral medication three times daily for 3 days.

Daily Fractionated Radiotherapy
In an active-controlled, double-blind trial in 135 patients receiving a 1-to 4-week course of fractionated radiotherapy (180 cGy doses) over a field size of greater than or equal to 100 cm^2 to the abdomen, ondansetron tablets was significantly more effective than prochlorperazine with respect to complete control of emesis (0 emetic episodes). Patients received the first dose of ondansetron tablets (8 mg) or prochlorperazine (10 mg) 1 to 2 hours before the first daily radiotherapy fraction, with subsequent 8 mg doses approximately every 8 hours on each day of radiotherapy.

14.3 Postoperative Nausea and Vomiting

In 2 placebo-controlled, double-blind trials (one conducted in the US and the other outside the US) in 865 females undergoing inpatient surgical procedures, ondansetron tablets 16 mg as a single dose or placebo was administered one hour before the induction of general balanced anesthesia (barbiturate, opioid, nitrous oxide, neuromuscular blockade, and supplemental isoflurane or enflurane), ondansetron tablets was significantly more effective than placebo in preventing postoperative nausea and vomiting.
No trials have been performed in males.

16 HOW SUPPLIED/STORAGE AND HANDLING

Ondansetron Tablets
Ondansetron Tablets USP, 4 mg (ondansetron hydrochloride dihydrate equivalent to 4 mg of ondansetron), are white, oval, film-coated tablets engraved with “4” on one side and “NO” on another side. They are supplied as follows:
NDC 45963-538-30 Bottles of 30
Ondansetron Tablets USP, 8 mg (ondansetron hydrochloride dihydrate equivalent to 8 mg of ondansetron), are yellow, oval, film-coated tablets engraved with “8” on one side and “NO” on the other side. They are supplied as follows:
NDC 45963-539-30 Bottles of 30
Store at 20° to 25°C (68° to 77°F). [See USP Controlled Room Temperature].

17 PATIENT COUNSELING INFORMATION

QT Prolongation
Inform patients that ondansetron tablets may cause serious cardiac arrhythmias such as QT prolongation. Instruct patients to tell their healthcare provider right away if they perceive a change in their heart rate, if they feel lightheaded, or if they have a syncopal episode.

Hypersensitivity Reactions
Inform patients that ondansetron tablets may cause hypersensitivity reactions, some as severe as anaphylaxis and bronchospasm. Instruct patients to immediately report any signs and symptoms of hypersensitivity reactions, including fever, chills, rash, or breathing problems to their healthcare provider.
Masking of Progressive Ileus and Gastric Distension
Inform patients following abdominal surgery or those with chemotherapy-induced nausea and vomiting that ondansetron tablets may mask signs and symptoms of bowel obstruction. Instruct patients to immediately report any signs or symptoms consistent with a potential bowel obstruction to their healthcare provider.

Drug Interactions

- Instruct the patient to report the use of all medications, especially apomorphine, to their healthcare provider. Concomitant use of apomorphine and ondansetron tablets may cause a significant drop in blood pressure and loss of consciousness.
- Advise patients of the possibility of serotonin syndrome with concomitant use of ondansetron tablets and another serotonergic agent such as medications to treat depression and migraines. Advise patients to seek immediate medical attention if the following symptoms occur: changes in mental status, autonomic instability, neuromuscular symptoms with or without gastrointestinal symptoms.

Distributed by:
Actavis Pharma Inc.,
Parsippany, NJ 07054 USA
Manufactured by:
Natco Pharma Limited
Kothur- 509 228, India